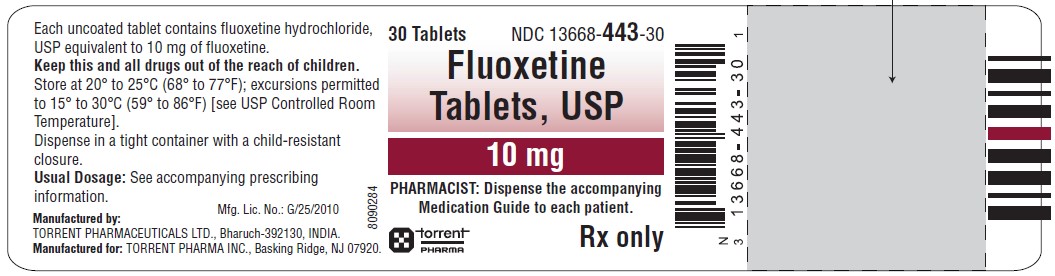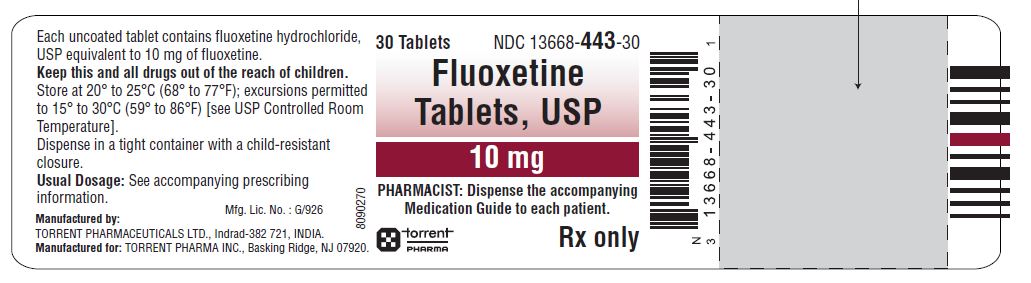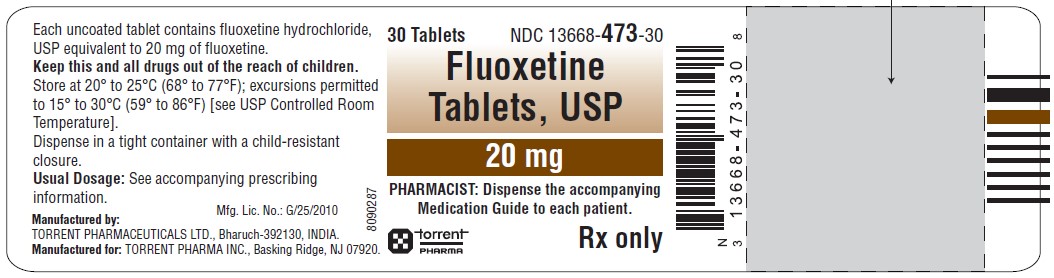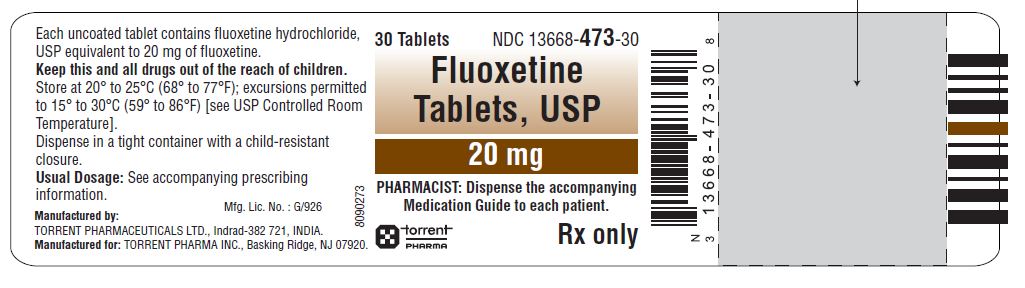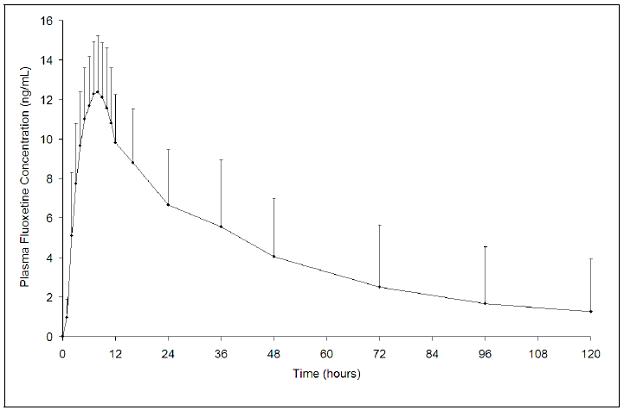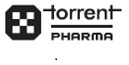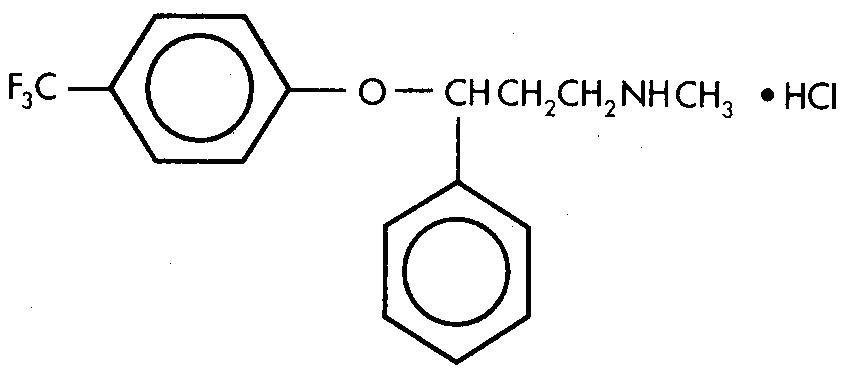 DRUG LABEL: Fluoxetine
NDC: 13668-443 | Form: TABLET
Manufacturer: Torrent Pharmaceuticals Limited
Category: prescription | Type: HUMAN PRESCRIPTION DRUG LABEL
Date: 20241211

ACTIVE INGREDIENTS: FLUOXETINE HYDROCHLORIDE 10 mg/1 1
INACTIVE INGREDIENTS: CELLULOSE, MICROCRYSTALLINE; CROSCARMELLOSE SODIUM; D&C YELLOW NO. 10; FD&C YELLOW NO. 6; MAGNESIUM STEARATE; POVIDONE K30; SILICON DIOXIDE

HIGHLIGHTS OF PRESCRIBING INFORMATION

These highlights do not include all the information needed to use FLUOXETINE TABLETS safely and effectively. See full prescribing information for FLUOXETINE TABLETS.
FLUOXETINE tablets, for oral use
Initial U.S. Approval:1987

BOXED WARNING

WARNING: SUICIDALITY AND ANTIDEPRESSANT DRUGS

See full prescribing information for complete boxed warning.

Increased risk of suicidal thinking and behavior in children, adolescents, and young adults taking antidepressants for Major Depressive Disorder (MDD) and other psychiatric disorders. Fluoxetine tablet is not approved for use in pediatric patients (5.1).

RECENT MAJOR CHANGES

Warnings and Precautions, Serotonin Syndrome (5.2) 06/2023

Warnings and Precautions (5.7) 06/2023

Warnings and Precautions, Sexual Dysfunction (5.15) 09/2021

1 INDICATIONS AND USAGE

Fluoxetine tablets, USP are selective serotonin reuptake inhibitor (SSRI) indicated for the treatment of Premenstrual Dysphoric Disorder (PMDD) (1.1)

2 DOSAGE AND ADMINISTRATION

- 20 mg/day continuously or intermittently (2.1)

3 DOSAGE FORMS AND STRENGTHS

- Tablets: 10 mg, 20 mg (3)

4 CONTRAINDICATIONS

- Serotonin Syndrome and MAOIs: Do not use with MAOIs intended to treat psychiatric disorders with fluoxetine tablet or within 5 weeks of stopping treatment with fluoxetine tablets. Do not use fluoxetine tablet within 14 days of stopping an MAIO intended to treat psychiatric disorders. In addition, do not start fluoxetine tablet in a patient who is being treated with linezolid or intravenous methylene blue (4.1)
- Do not use with pimozide due to risk of drug interaction or QTc prolongation (4.2, 7.9)
- Do not use with thioridazine due to QTc interval prolongation or potential for elevated thioridazine plasma levels. Do not use thioridazine within 5 weeks of discontinuing fluoxetine tablet (4.2, 7.9)

5 WARNINGS AND PRECAUTIONS

- Clinical Worsening and Suicide Risk: Monitor for clinical worsening and suicidal thinking and behavior (5.1)
- Serotonin Syndrome: Serotonin syndrome has been reported with SSRIs and SNRIs, including fluoxetine hydrochloride, both when taken alone, but especially when co-administered with other serotonergic agents. If such symptoms occur, discontinue fluoxetine tablet and serotonergic agents and initiate supportive treatment. If concomitant use of fluoxetine hydrochloride with other serotonergic drugs is clinically warranted, patients should be made aware of a potential increased risk for serotonin syndrome, particularly during treatment initiation and dose increases (5.2)
- Allergic Reactions and Rash: Discontinue upon appearance of rash or allergic phenomena (5.3)
- Activation of Mania/Hypomania: Screen for Bipolar Disorder and monitor for mania/hypomania (5.4)
- Seizures: Use cautiously in patients with a history of seizures or with conditions that potentially lower the seizure threshold (5.5)
- Altered Appetite and Weight: Significant weight loss has occurred (5.6)
- Abnormal Bleeding: May increase the risk of bleeding. Use with NSAIDs, aspirin, warfarin, or drugs that affect coagulation may potentiate the risk of gastrointestinal or other bleeding (5.7)
- Angle-Closure Glaucoma: Angle-closure glaucoma has occurred in patients who have untreated anatomically narrow angles and who are treated with antidepressants (5.8)
- Hyponatremia: Has been reported with fluoxetine in association with syndrome of inappropriate antidiuretic hormone (SIADH) (5.9)
- Anxiety and Insomnia: May occur (5.10)
- Potential for Cognitive and Motor Impairment: Has potential to impair judgment, thinking, and motor skills. Use caution when operating machinery (5.12)
- Long Half-Life: Changes in dose will not be fully reflected in plasma for several weeks (5.13)
- Sexual dysfunction: Fluoxetine tablets use may cause symptoms of sexual dysfunction (5.15)

6 ADVERSE REACTIONS

Most common adverse reactions (incidence rate greater than or equal to 5% and greater than placebo) associated with fluoxetine tablet 20 mg (either continuous or intermittent) for PMDD:

Headache, asthenia, pain, accidental injury, infection, flu syndrome, nausea, diarrhea, insomnia, dizziness, nervousness, thinking abnormal, libido decreased, rhinitis, and pharyngitis (6.1).

To report SUSPECTED ADVERSE REACTIONS, contact Torrent Pharma Inc. at 1-800-912-9561 or FDA at 1-800-FDA-1088 or www.fda.gov/medwatch.

7 DRUG INTERACTIONS

- Monoamine Oxidase Inhibitors (MAOI): Fluoxetine is contraindicated for use with MAOI's, or within 14 days of discontinuing an MAOI due to risk of drug interaction. At least 5 weeks should be allowed after stopping fluoxetine before starting treatment with an MAOI (4, 7.1)
- Pimozide: Fluoxetine is contraindicated for use with pimozide due to risk of drug interaction or QTc prolongation (4, 7.9)
- Thioridazine: Fluoxetine is contraindicated for use with thioridazine due to QTc interval prolongation or potential for elevated thioridazine plasma levels. Do not use thioridazine within 5 weeks of discontinuing fluoxetine tablet. (4, 7.9)
- Drugs Metabolized by CYP2D6: Fluoxetine is a potent inhibitor of CYP2D6 enzyme pathway (7.9)
- Tricyclic Antidepressants (TCAs): Monitor TCA levels during coadministration with fluoxetine hydrochloride or when fluoxetine hydrochloride has been recently discontinued (7.9)
- CNS Acting Drugs: Caution should be used when taken in combination with other centrally acting drugs (7.2)
- Benzodiazepines: Diazepam – increased t½ , alprazolam - further psychomotor performance decrement due to increased levels (7.9)
- Antipsychotics: Potential for elevation of haloperidol and clozapine levels (7.9)
- Anticonvulsants: Potential for elevated phenytoin and carbamazepine levels and clinical anticonvulsant toxicity (7.9)
- Serotonergic Drugs: Potential for Serotonin Syndrome (5.2, 7.3)
- Triptans: There have been rare post marketing reports of Serotonin Syndrome with use of an SSRI and a triptan (5.2, 7.4)
- Tryptophan: Concomitant use with tryptophan is not recommended (5.2, 7.5)
- Drugs that Interfere with Hemostasis (for example, NSAIDs, Aspirin, Warfarin): May potentiate the risk of bleeding (7.6)
- Drugs Tightly Bound to Plasma Proteins: May cause a shift in plasma concentrations (7.8, 7.9)

8 USE IN SPECIFIC POPULATIONS

- Pregnancy: PMDD does not exist during pregnancy. Fluoxetine should be used during pregnancy only if the potential benefit justifies the potential risks to the fetus (8.1)
- Nursing Mothers: Breast feeding is not recommended (8.3)
- Hepatic Impairment: Lower or less frequent dosing may be appropriate in patients with cirrhosis (8.6)

FULL PRESCRIBING INFORMATION

BOXED WARNING

WARNING: SUICIDALITY AND ANTIDEPRESSANT DRUGS

Antidepressants increased the risk compared to placebo of suicidal thinking and behavior (suicidality) in children, adolescents, and young adults in short-term studies of Major Depressive Disorder (MDD) and other psychiatric disorders. Anyone considering the use of fluoxetine tablet or any other antidepressant in a child, adolescent, or young adult must balance this risk with the clinical need. Short-term studies did not show an increase in the risk of suicidality with antidepressants compared to placebo in adults beyond age 24; there was a reduction in risk with antidepressants compared to placebo in adults aged 65 and older. Depression and certain other psychiatric disorders are themselves associated with increases in the risk of suicide. Patients of all ages who are started on antidepressant therapy should be monitored appropriately and observed closely for clinical worsening, suicidality, or unusual changes in behavior. Families and caregivers should be advised of the need for close observation and communication with the prescriber. Fluoxetine tablet is not approved for use in pediatric patients [see Warnings and Precautions (5.1) and Use in Specific Populations (8.4)].

1 INDICATIONS AND USAGE

1.1 Premenstrual Dysphoric Disorder (PMDD)

Fluoxetine tablets, USP are indicated for the treatment of premenstrual dysphoric disorder (PMDD) [see Clinical Studies (14.1)].

The effectiveness of fluoxetine tablets, USP in long-term use (that is, for more than 6 months) has not been systematically evaluated in placebo-controlled trials. The use of fluoxetine tablets, USP for extended periods should be periodically re-evaluated for the individual patient [see Dosage and Administration (2.1)].

2 DOSAGE AND ADMINISTRATION

2.1 Treatment

The recommended dose of fluoxetine tablets for the treatment of PMDD is 20 mg/day given continuously (every day of the menstrual cycle) or intermittently (defined as starting a daily dose 14 days prior to the anticipated onset of menstruation through the first full day of menses and repeating with each new cycle). The dosing regimen should be based on individual patient characteristics. In a study comparing continuous dosing of fluoxetine 20 and 60 mg/day to placebo, both doses were proven to be effective, but there was no statistically significant added benefit for the 60 mg/day compared with the 20 mg/day dose. Fluoxetine doses above 60 mg/day have not been systematically studied in patients with PMDD. The maximum fluoxetine dose should not exceed 80 mg/day [see Clinical Studies (14.1)].

Systematic evaluation of fluoxetine tablets has shown that its efficacy in PMDD is maintained for periods of up to 6 months at a dose of 20 mg/day given continuously and up to 3 months at a dose of 20 mg/day given intermittently [see Clinical Studies (14.1)]. Patients should be periodically re-assessed to determine the need for continued treatment.

2.2 Dosing in Specific Populations

Treatment of Pregnant Women — PMDD does not exist in pregnancy. However, if there is a need to treat pregnant women with fluoxetine, the physician should carefully consider the potential risks and potential benefits of treatment. Neonates exposed to SSRIs or SNRIs late in the third trimester have developed complications requiring prolonged hospitalization, respiratory support, and tube feeding [see Use in Specific Populations (8.1)].

Hepatic Impairment — A lower or less frequent dosage should be used in patients with hepatic impairment [see Clinical Pharmacology (12.3) and Use in Specific Populations (8.6)].

Concomitant Illness — Patients with concurrent disease or on multiple concomitant medications may require dosage adjustments [see Warnings and Precautions (5.11) and Clinical Pharmacology (12.3)].

2.3 Discontinuation of Treatment

Symptoms associated with discontinuation of fluoxetine, SNRIs, and SSRIs, have been reported [see Warnings and Precautions (5.14)].

2.4 Switching a Patient To or From a Monoamine Oxidase Inhibitor (MAOI) Intended to Treat Psychiatric Disorders

At least 14 days should elapse between discontinuation of an MAOI intended to treat psychiatric disorders and initiation of therapy with fluoxetine tablets. Conversely, at least 5 weeks should be allowed after stopping fluoxetine tablets before starting an MAOI intended to treat psychiatric disorders [see Contraindications (4.1)].

2.5 Use of Fluoxetine Tablets with Other MAOIs such as Linezolid or Methylene Blue

Do not start fluoxetine tablets in a patient who is being treated with linezolid or intravenous methylene blue because there is an increased risk of serotonin syndrome. In a patient who requires more urgent treatment of a psychiatric condition, other interventions, including hospitalization, should be considered [see Contraindications (4.1)].

In some cases, a patient already receiving fluoxetine tablets therapy may require urgent treatment with linezolid or intravenous methylene blue. If acceptable alternatives to linezolid or intravenous methylene blue treatment are not available and the potential benefits of linezolid or intravenous methylene blue treatment are judged to outweigh the risks of serotonin syndrome in a particular patient, fluoxetine tablets should be stopped promptly, and linezolid or intravenous methylene blue can be administered. The patient should be monitored for symptoms of serotonin syndrome for five weeks or until 24 hours after the last dose of linezolid or intravenous methylene blue, whichever comes first. Therapy with fluoxetine tablets may be resumed 24 hours after the last dose of linezolid or intravenous methylene blue [see Warnings and Precautions (5.2)].

The risk of administering methylene blue by non-intravenous routes (such as oral tablets or by local injection) or in intravenous doses much lower than 1 mg/kg with fluoxetine tablets is unclear. The clinician should, nevertheless, be aware of the possibility of emergent symptoms of serotonin syndrome with such use [see Warnings and Precautions (5.2)].

3 DOSAGE FORMS AND STRENGTHS

- 10 mg tablet is a light cream to cream colored, flat round, uncoated tablets with beveled edges, debossed with "43" on one side and plain on other side.
- 20 mg tablet is a light yellow to yellow colored, flat round, uncoated tablets with beveled edges, debossed with "73" on one side and plain on other side.

4 CONTRAINDICATIONS

4.1 Monoamine Oxidase Inhibitors

The use of MAOIs intended to treat psychiatric disorders with fluoxetine tablet or within 5 weeks of stopping treatment with fluoxetine tablet is contraindicated because of an increased risk of serotonin syndrome. The use of fluoxetine tablet within 14 days of stopping an MAOI intended to treat psychiatric disorders is also contraindicated [see Dosage and Administration (2.4) and Warnings and Precautions (5.2)].

Starting fluoxetine tablet in a patient who is being treated with MAOIs such as linezolid or intravenous methylene blue is also contraindicated because of an increased risk of serotonin syndrome [see Dosage and Administration (2.5) and Warnings and Precautions (5.2)].

4.2 Other Contraindications

The use of fluoxetine hydrochloride is contraindicated with the following:

- Pimozide [see Drug Interactions (7.9)]
- Thioridazine [see Drug Interactions (7.9)]

5 WARNINGS AND PRECAUTIONS

5.1 Clinical Worsening and Suicide Risk

Patients with Major Depressive Disorder (MDD), both adult and pediatric, may experience worsening of their depression and/or the emergence of suicidal ideation and behavior (suicidality) or unusual changes in behavior, whether or not they are taking antidepressant medications, and this risk may persist until significant remission occurs. Suicide is a known risk of depression and certain other psychiatric disorders, and these disorders themselves are the strongest predictors of suicide. There has been a long-standing concern, however, that antidepressants may have a role in inducing worsening of depression and the emergence of suicidality in certain patients during the early phases of treatment. Pooled analyses of short-term placebo-controlled trials of antidepressant drugs (SSRIs and others) showed that these drugs increase the risk of suicidal thinking and behavior (suicidality) in children, adolescents, and young adults (ages 18 to 24) with Major Depressive Disorder (MDD) and other psychiatric disorders. Short-term studies did not show an increase in the risk of suicidality with antidepressants compared to placebo in adults beyond age 24; there was a reduction with antidepressants compared to placebo in adults aged 65 and older.

The pooled analyses of placebo-controlled trials in children and adolescents with MDD, Obsessive Compulsive Disorder (OCD), or other psychiatric disorders included a total of 24 short-term trials of 9 antidepressant drugs in over 4,400 patients. The pooled analyses of placebo-controlled trials in adults with MDD or other psychiatric disorders included a total of 295 short-term trials (median duration of 2 months) of 11 antidepressant drugs in over 77,000 patients. There was considerable variation in risk of suicidality among drugs, but a tendency toward an increase in the younger patients for almost all drugs studied. There were differences in absolute risk of suicidality across the different indications, with the highest incidence in MDD. The risk differences (drug versus placebo), however, were relatively stable within age strata and across indications. These risk differences (drug-placebo difference in the number of cases of suicidality per 1,000 patients treated) are provided in Table 1.

Table 1: Suicidality per 1,000 Patients Treated

Age Range | Drug-Placebo Difference in Number of Cases of Suicidality per 1,000 Patients Treated
 | Increases Compared to Placebo
<18 | 14 additional cases
18 to 24 | 5 additional cases
 | Decreases Compared to Placebo
25 to 64 | 1 fewer case
≥65 | 6 fewer cases

No suicides occurred in any of the pediatric trials. There were suicides in the adult trials, but the number was not sufficient to reach any conclusion about drug effect on suicide.

It is unknown whether the suicidality risk extends to longer-term use, that is, beyond several months. However, there is substantial evidence from placebo-controlled maintenance trials in adults with depression that the use of antidepressants can delay the recurrence of depression.

All patients being treated with antidepressants for any indication should be monitored appropriately and observed closely for clinical worsening, suicidality, and unusual changes in behavior, especially during the initial few months of a course of drug therapy, or at times of dose changes, either increases or decreases.

The following symptoms, anxiety, agitation, panic attacks, insomnia, irritability, hostility, aggressiveness, impulsivity, akathisia (psychomotor restlessness), hypomania, and mania, have been reported in adult and pediatric patients being treated with antidepressants for Major Depressive Disorder as well as for other indications, both psychiatric and nonpsychiatric. Although a causal link between the emergence of such symptoms and either the worsening of depression and/or the emergence of suicidal impulses has not been established, there is concern that such symptoms may represent precursors to emerging suicidality.

Consideration should be given to changing the therapeutic regimen, including possibly discontinuing the medication, in patients whose depression is persistently worse, or who are experiencing emergent suicidality or symptoms that might be precursors to worsening depression or suicidality, especially if these symptoms are severe, abrupt in onset, or were not part of the patient’s presenting symptoms.

If the decision has been made to discontinue treatment, medication should be tapered, as rapidly as is feasible, but with recognition that abrupt discontinuation can be associated with certain symptoms [see Warnings and Precautions (5.14)].

Families and caregivers of patients being treated with antidepressants for Major Depressive Disorder or other indications, both psychiatric and nonpsychiatric, should be alerted about the need to monitor patients for the emergence of agitation, irritability, unusual changes in behavior, and the other symptoms described above, as well as the emergence of suicidality, and to report such symptoms immediately to health care providers. Such monitoring should include daily observation by families and caregivers. Prescriptions for fluoxetine tablet should be written for the smallest quantity of tablets consistent with good patient management, in order to reduce the risk of overdose.

It should be noted that fluoxetine tablet is not approved for treating any indication in the pediatric population.

5.2 Serotonin Syndrome

The development of a potentially life-threatening serotonin syndrome has been reported with SNRIs and SSRIs, including fluoxetine hydrochloride, alone but particularly with concomitant use of other serotonergic drugs (including triptans, tricyclic antidepressants, fentanyl, lithium, tramadol, meperidine, methadone, tryptophan, buspirone, amphetamines, and St. John's Wort) and with drugs that impair metabolism of serotonin (in particular, MAOIs, both those intended to treat psychiatric disorders and also others, such as linezolid and intravenous methylene blue).

Serotonin syndrome symptoms may include mental status changes (for example, agitation, hallucinations, delirium, and coma), autonomic instability (for example, tachycardia, labile blood pressure, dizziness, diaphoresis, flushing, hyperthermia), neuromuscular symptoms (for example, tremor, rigidity, myoclonus, hyperreflexia, incoordination), seizures, and/or gastrointestinal symptoms (for example, nausea, vomiting, diarrhea). Patients should be monitored for the emergence of serotonin syndrome.

The concomitant use of fluoxetine tablet with MAOIs intended to treat psychiatric disorders is contraindicated. Fluoxetine tablet should also not be started in a patient who is being treated with MAOIs such as linezolid or intravenous methylene blue. All reports with methylene blue that provided information on the route of administration involved intravenous administration in the dose range of 1mg/kg to 8 mg/kg. No reports involved the administration of methylene blue by other routes (such as oral tablets or local tissue injection) or at lower doses. There may be circumstances when it is necessary to initiate treatment with an MAOI such as linezolid or intravenous methylene blue in a patient taking fluoxetine tablet. Fluoxetine tablet should be discontinued before initiating treatment with the MAOI [see Contraindications (4.1) and Dosage and Administration (2.5)].

If concomitant use of fluoxetine hydrochloride with other serotonergic drugs, that is, triptans, tricyclic antidepressants, fentanyl, lithium, tramadol, buspirone, amphetamines, tryptophan and St. John's Wort is clinically warranted, patients should be made aware of a potential increased risk for serotonin syndrome, particularly during treatment initiation and dose increases.

Treatment with fluoxetine hydrochloride and any concomitant serotonergic agents, should be discontinued immediately if the above events occur and supportive symptomatic treatment should be initiated.

5.3 Allergic Reactions and Rash

In 4 clinical trials for PMDD, 4% of 415 patients treated with fluoxetine tablet reported rash and/or urticaria. None of these cases were classified as serious and 2 of 415 patients (both receiving 60 mg) were withdrawn from treatment because of rash and/or urticaria.

In US fluoxetine clinical trials for conditions other than PMDD, 7% of 10,782 patients developed various types of rashes and/or urticaria. Among the cases of rash and/or urticaria reported in premarketing clinical trials, almost a third were withdrawn from treatment because of the rash and/or systemic signs or symptoms associated with the rash. Clinical findings reported in association with rash include fever, leukocytosis, arthralgias, edema, carpal tunnel syndrome, respiratory distress, lymphadenopathy, proteinuria, and mild transaminase elevation. Most patients improved promptly with discontinuation of fluoxetine and/or adjunctive treatment with antihistamines or steroids, and all patients experiencing these reactions were reported to recover completely.

In premarketing clinical trials for conditions other than PMDD, 2 patients are known to have developed a serious cutaneous systemic illness. In neither patient was there an unequivocal diagnosis, but one was considered to have a leukocytoclastic vasculitis, and the other, a severe desquamating syndrome that was considered variously to be a vasculitis or erythema multiforme. Other patients have had systemic syndromes suggestive of serum sickness.

Since the introduction of fluoxetine, systemic reactions, possibly related to vasculitis and including lupus-like syndrome, have developed in patients with rash. Although these reactions are rare, they may be serious, involving the lung, kidney, or liver. Death has been reported to occur in association with these systemic reactions.

Anaphylactoid reactions, including bronchospasm, angioedema, laryngospasm, and urticaria alone and in combination, have been reported.

Pulmonary reactions, including inflammatory processes of varying histopathology and/or fibrosis, have been reported rarely. These reactions have occurred with dyspnea as the only preceding symptom.

Whether these systemic reactions and rash have a common underlying cause or are due to different etiologies or pathogenic processes is not known. Furthermore, a specific underlying immunologic basis for these reactions has not been identified. Upon the appearance of rash or of other possibly allergic phenomena for which an alternative etiology cannot be identified, fluoxetine tablets should be discontinued.

5.4 Screening Patients for Bipolar Disorder and Monitoring for Mania/Hypomania

A major depressive episode may be the initial presentation of Bipolar Disorder. It is generally believed (though not established in controlled trials) that treating such an episode with an antidepressant alone may increase the likelihood of precipitation of a mixed/manic episode in patients at risk for Bipolar Disorder. Whether any of the symptoms described for clinical worsening and suicide risk represent such a conversion is unknown. However, prior to initiating treatment with an antidepressant, patients with depressive symptoms should be adequately screened to determine if they are at risk for Bipolar Disorder; such screening should include a detailed psychiatric history, including a family history of suicide, Bipolar Disorder, and depression. It should be noted that fluoxetine tablet is not indicated for the treatment of depressive episodes associated with Bipolar I Disorder.

No patients treated with fluoxetine tablet in 4 PMDD clinical trials (N = 415) reported mania/hypomania. In all US fluoxetine clinical trials for conditions other than PMDD, 0.7% of 10,782 patients reported mania/hypomania. Activation of mania/hypomania may occur with medications used to treat depression, especially in patients predisposed to Bipolar I Disorder.

5.5 Seizures

No patients treated with fluoxetine tablet in 4 PMDD clinical trials (N = 415) reported seizures. In all US fluoxetine clinical trials for conditions other than PMDD, 0.2% of 10,782 patients reported convulsions. Fluoxetine hydrochloride should be introduced with care in patients with a history of seizures.

5.6 Altered Appetite and Weight

In 2 placebo-controlled clinical trials for PMDD, patients treated with fluoxetine tablets reported changes in appetite and weight [see Table 2]. For individual rates for fluoxetine tablets 20 mg given as continuous and intermittent dosing, see Table 4 and accompanying footnote [see Adverse Reactions (6.1)].

Table 2: Altered Appetite and Weight Treatment Emergent Adverse Reactions: Incidence in PMDD Placebo-Controlled Clinical Trials
 | Percentage of Patients Reporting Adverse Reaction
Treatment Emergent Adverse Reaction | 20 mg (continuous and intermittent pooled) | 60 mg (continuous) | Placebo (pooled)
Anorexia (decreased appetite) | 4% | 13% | 2%
Weight Loss (≥7%) | 7% | 12% | 3%
Weight Gain (≥7%) | 8% | 6% | 1%

In US placebo-controlled clinical trials of fluoxetine for other approved indications, changes in appetite and weight have also been reported [see Adverse Reactions (6.1) Table 5].

5.7 Abnormal Bleeding

SNRIs and SSRIs, including fluoxetine, may increase the risk of bleeding reactions. Concomitant use of aspirin, nonsteroidal anti-inflammatory drugs, warfarin, and other anti-coagulants may add to this risk. Case reports and epidemiological studies (case-control and cohort design) have demonstrated an association between use of drugs that interfere with serotonin reuptake and the occurrence of gastrointestinal bleeding. Based on data from the published observational studies, exposure to SSRIs, particularly in the month before delivery, has been associated with a less than 2-fold increase in the risk of postpartum hemorrhage [see Use in Specific Populations (8.1)]. Bleeding reactions related to SNRIs and SSRIs use have ranged from ecchymoses, hematomas, epistaxis, and petechiae to life-threatening hemorrhages.

Patients should be cautioned about the increased risk of bleeding associated with the concomitant use of fluoxetine and NSAIDs, aspirin, warfarin, or other drugs that affect coagulation [see Drug Interactions (7.6)].

5.8 Angle-Closure Glaucoma

The pupillary dilation that occurs following use of many antidepressants and fluoxetine may trigger an angle closure attack in a patient with anatomically narrow angles who does not have a patent iridectomy.

5.9 Hyponatremia

Hyponatremia has been reported during treatment with SNRIs and SSRIs, including fluoxetine. In many cases, this hyponatremia appears to be the result of the syndrome of inappropriate antidiuretic hormone secretion (SIADH). Cases with serum sodium lower than 110 mmol/L have been reported and appeared to be reversible when fluoxetine was discontinued. Elderly patients may be at greater risk of developing hyponatremia with SNRIs and SSRIs. Also, patients taking diuretics or who are otherwise volume depleted may be at greater risk [see Use in Specific Populations (8.5)]. Discontinuation of fluoxetine tablet should be considered in patients with symptomatic hyponatremia and appropriate medical intervention should be instituted.

Signs and symptoms of hyponatremia include headache, difficulty concentrating, memory impairment, confusion, weakness, and unsteadiness, which may lead to falls. More severe and/or acute cases have been associated with hallucination, syncope, seizure, coma, respiratory arrest, and death.

5.10 Anxiety and Insomnia

In 2 placebo-controlled clinical trials for PMDD, patients treated with fluoxetine tablet reported anxiety, nervousness, and insomnia [see Table 3].

For individual rates of anxiety, nervousness, and insomnia with fluoxetine tablet 20 mg given as continuous or intermittent dosing, see Table 5 and accompanying footnote [see Adverse Reactions (6.1)].

Table 3: Anxiety and Insomnia Treatment Emergent Adverse Reactions: Incidence in PMDD Placebo-Controlled Clinical Trials
 | Percentage of Patients Reporting Adverse Reaction
Treatment Emergent Adverse Reaction | 20 mg (continuous and intermittent pooled) | 60 mg (continuous) | Placebo (pooled)
Anxiety | 3% | 9% | 4%
Nervousness | 5% | 9% | 3%
Insomnia | 9% | 26% | 7%

Anxiety, nervousness, and insomnia were associated with discontinuation for fluoxetine tablet [see Table 4 and Warnings and Precautions (5.14)].

Table 4: Anxiety, Nervousness, and Insomnia: Treatment Discontinuation Rates in PMDD Placebo-Controlled Clinical Trials
 | Percentage of Patient Discontinuation due to Adverse Reaction
Treatment Emergent Adverse Reaction | 20 mg (continuous and intermittent pooled) | 60 mg (continuous) | Placebo (pooled)
Anxiety | 0% | 6% | 1%
Nervousness | 1% | 0% | 0.5%
Insomnia | 1% | 4% | 0.5%

In US placebo-controlled clinical trials of fluoxetine for other approved indications, anxiety, nervousness, and insomnia have been among the most commonly reported adverse reactions [see Table 6 and Adverse Reactions (6.1)].

5.11 Use in Patients with Concomitant Illness

Clinical experience with fluoxetine in patients with concomitant systemic illness is limited. Caution is advisable in using fluoxetine in patients with diseases or conditions that could affect metabolism or hemodynamic responses.

Cardiovascular — Fluoxetine has not been evaluated or used to any appreciable extent in patients with a recent history of myocardial infarction or unstable heart disease. Patients with these diagnoses were systematically excluded from clinical studies during the product's premarket testing. However, the electrocardiograms of 312 patients who received fluoxetine in double-blind trials, for a condition other than PMDD, were retrospectively evaluated; no conduction abnormalities that resulted in heart block were observed. The mean heart rate was reduced by approximately 3 beats/min.

Glycemic Control — In patients with diabetes, fluoxetine may alter glycemic control. Hypoglycemia has occurred during therapy with fluoxetine, and hyperglycemia has developed following discontinuation of the drug. As is true with many other types of medication when taken concurrently by patients with diabetes, insulin and/or oral hypoglycemic, dosage may need to be adjusted when therapy with fluoxetine is instituted or discontinued.

5.12 Potential for Cognitive and Motor Impairment

Fluoxetine hydrochloride has the potential to impair judgment, thinking, or motor skills. Patients should be cautioned about operating hazardous machinery, including automobiles, until they are reasonably certain that the drug treatment does not affect them adversely.

5.13 Long Elimination Half-Life

Because of the long elimination half-lives of the parent drug and its major active metabolite, changes in dose will not be fully reflected in plasma for several weeks, affecting both strategies for titration to final dose and withdrawal from treatment. This is of potential consequence when drug discontinuation is required or when drugs are prescribed that might interact with fluoxetine and norfluoxetine following the discontinuation of fluoxetine [see Clinical Pharmacology (12.3) and Drug Interactions (7)].

5.14 Discontinuation of Treatment

During marketing of fluoxetine tablet, SNRIs, and SSRIs, there have been spontaneous reports of adverse reactions occurring upon discontinuation of these drugs, particularly when abrupt, including the following: dysphoric mood, irritability, agitation, dizziness, sensory disturbances (for example, paresthesias such as electric shock sensations), anxiety, confusion, headache, lethargy, emotional lability, insomnia, and hypomania. While these reactions are generally self-limiting, there have been reports of serious discontinuation symptoms.

Patients should be monitored for these symptoms when discontinuing treatment with fluoxetine tablet. A gradual reduction in the dose rather than abrupt cessation is recommended whenever possible. If intolerable symptoms occur following a decrease in the dose or upon discontinuation of treatment, then resuming the previously prescribed dose may be considered. Subsequently, the dose may continue to be decreased but at a more gradual rate. Plasma fluoxetine and norfluoxetine concentration decrease gradually at the conclusion of therapy which may minimize the risk of discontinuation symptoms with this drug.

5.15 Sexual Dysfunction

Use of SSRIs, including fluoxetine tablets, may cause symptoms of sexual dysfunction [see Adverse Reactions (6.1, 6.2)]. In female patients, SSRI/SNRI use may result in decreased libido and delayed or absent orgasm.

It is important for prescribers to inquire about sexual function prior to initiation of fluoxetine tablets and to inquire specifically about changes in sexual function during treatment, because sexual function may not be spontaneously reported. When evaluating changes in sexual function, obtaining a detailed history (including timing of symptom onset) is important because sexual symptoms may have other causes, including the underlying psychiatric disorder. Discuss potential management strategies to support patients in making informed decisions about treatment.

6 ADVERSE REACTIONS

6.1 Clinical Trials Experience

Because clinical trials are conducted under widely varying conditions, adverse reaction rates observed in the clinical trials of a drug cannot be directly compared to rates in the clinical trials of another drug and may not reflect or predict the rates observed in practice.

Multiple doses of fluoxetine have been administered to 10,782 patients with various diagnoses in US clinical trials. Adverse reactions were recorded by clinical investigators using descriptive terminology of their own choosing. Consequently, it is not possible to provide a meaningful estimate of the proportion of individuals experiencing adverse reactions without first grouping similar types of reactions into a limited (that is, reduced) number of standardized reaction categories.

In the tables and tabulations that follow, COSTART Dictionary terminology has been used to classify reported adverse reactions. The stated frequencies represent the proportion of individuals who experienced, at least once, a treatment-emergent adverse reaction of the type listed. A reaction was considered treatment-emergent if it occurred for the first time or worsened while receiving therapy following baseline evaluation. It is important to emphasize that reactions reported during therapy were not necessarily caused by it.

The prescriber should be aware that the figures in the tables and tabulations cannot be used to predict the incidence of side effects in the course of usual medical practice where patient characteristics and other factors differ from those that prevailed in the clinical trials. Similarly, the cited frequencies cannot be compared with figures obtained from other clinical investigations involving different treatments, uses, and investigators. The cited figures, however, do provide the prescribing physician with some basis for estimating the relative contribution of drug and nondrug factors to the side effect incidence rate in the population studied.

Incidence in placebo-controlled PMDD clinical trials — In 1 of 3 placebo-controlled, continuous-dosing trials and 1 placebo-controlled, intermittent-dosing trial of fluoxetine in PMDD, treatment-emergent adverse reactions reporting rates were assessed. The information contained in Table 5 enumerates the most common treatment-emergent adverse reactions associated with the use of fluoxetine tablet 20 mg (incidence of at least 5% for fluoxetine tablet 20 mg and greater than placebo) for the treatment of PMDD and is based on data from the continuous-dosing trial at the recommended dose of fluoxetine tablet (fluoxetine tablets 20 mg, N = 104; placebo, N = 108) and data from the intermittent-dosing trial of fluoxetine in PMDD (fluoxetine tablets 20 mg, N = 86; placebo, N = 88).

Table 5: Most Common Treatment-Emergent Adverse Reactions: Incidence in PMDD Placebo-Controlled Clinical Trials
 | Percentage of Patients Reporting Adverse Reaction
Body System/Adverse Reaction^1 | Fluoxetine tablet 20 mg/day Continuously (N = 104) | Fluoxetine tablet 20 mg/day Intermittently (N = 86) | Placebo (Pooled) (N = 196)
Body as a Whole
Headache | 13 | 15 | 11
Asthenia | 12 | 8 | 4
Pain | 9 | 3 | 7
Accidental injury | 8 | 1 | 5
Infection | 7 | 0 | 3
Flu syndrome | 12 | 3 | 7
Digestive System
Nausea | 13 | 9 | 6
Diarrhea | 6 | 2 | 6
Nervous System
Insomnia | 9 | 10 | 7
Dizziness | 7 | 2 | 3
Nervousness | 7 | 3 | 3
Thinking abnormal^2 | 6 | 5 | 0
Libido decreased | 3 | 9 | 1
Respiratory System
Rhinitis | 23 | 16 | 15
Pharyngitis | 10 | 6 | 5
^1Included in the table are adverse reactions reported by at least 5% of patients taking fluoxetine tablet 20 mg either continuously or intermittently. For additional adverse reaction terms referenced in Warnings and Precautions, reporting rates for fluoxetine tablet 20 mg continuous and intermittent were, respectively: anxiety 4.8%, 1.2% and anorexia 3.8%, 3.5%.
^2Thinking abnormal is the COSTART term that captures concentration difficulties.

Incidence in US depression, OCD, and bulimia placebo-controlled clinical trials (excluding data from extensions of trials) — Table 6 enumerates the most common treatment-emergent adverse reactions associated with the use of fluoxetine up to 80 mg (incidence of at least 2% for fluoxetine and greater than placebo) in female patients ages 18 to 45 years from US placebo-controlled clinical trials in the treatment of depression, OCD, and bulimia.

Table 6: Treatment-Emergent Adverse Reactions: Incidence in Female Patients Ages 18 to 45 Years in Depression, OCD, and Bulimia Placebo-Controlled US Clinical Trials
 | Percentage of Patients Reporting Adverse Reaction
Body System/Adverse Reaction^1 | Fluoxetine (N = 1,145) | Placebo (N = 553)
Body as a Whole
Headache | 24 | 21
Asthenia | 14 | 6
Flu syndrome | 7 | 3
Abdominal pain | 6 | 5
Accidental injury | 4 | 3
Fever | 3 | 2
Cardiovascular System
Palpitation | 3 | 2
Vasodilatation | 3 | 1
Digestive System
Nausea | 27 | 11
Anorexia | 11 | 4
Dry mouth | 11 | 8
Diarrhea | 10 | 7
Dyspepsia | 7 | 5
Constipation | 5 | 3
Vomiting | 3 | 2
Metabolic and Nutritional Disorders
Weight loss | 3 | 1
Nervous System
Insomnia | 24 | 11
Nervousness | 14 | 10
Anxiety | 13 | 9
Somnolence | 13 | 6
Tremor | 12 | 1
Dizziness | 11 | 5
Libido decreased | 4 | 1
Abnormal dreams | 3 | 2
Thinking abnormal^2 | 3 | 2
Respiratory System
Pharyngitis | 6 | 5
Yawn | 5 | -
Skin and Appendages Skin and Subcutaneous Tissue Disorders
Sweating | 8 | 3
Rash | 5 | 3
Special Senses
Abnormal vision | 3 | 1
Urogenital System
Urinary frequency | 2 | 1
^1Included are reactions reported by at least 2% of patients taking fluoxetine, except the following adverse reactions, which had an incidence on placebo greater than fluoxetine (depression, OCD, and bulimia combined): back pain, cough increased, depression (includes suicidal thoughts), dysmenorrhea, flatulence, infection, myalgia, pain, pruritus, rhinitis, sinusitis.
^2Thinking abnormal is the COSTART term that captures concentration difficulties.
Incidence less than 0.5%.

Adverse reactions associated with discontinuation in two placebo-controlled PMDD clinical trials — In a continuous-dosing PMDD placebo-controlled trial, the most common adverse reaction (incidence at least 2% for fluoxetine tablet 20 mg and greater than placebo) associated with discontinuation was nausea (3% for fluoxetine tablet 20 mg, N = 104 and 1% for placebo, N = 108). In an intermittent-dosing placebo-controlled trial, no reactions associated with discontinuation reached an incidence of 2% for fluoxetine tablet 20 mg. In these clinical trials, more than one reaction may have been recorded as the cause of discontinuation.

Adverse reactions associated with discontinuation in depression, OCD, and bulimia placebo-controlled US clinical trials (excluding data from extensions of trials) — In female patients age 18 to 45 years in US depression, OCD, and bulimia placebo-controlled clinical trials combined, which collected a single primary reaction associated with discontinuation (incidence at least 1% for fluoxetine and at least twice that for placebo), insomnia (1%, N = 561) was the only reaction reported.

Female sexual dysfunction with SSRIs — Although changes in sexual desire, sexual performance, and sexual satisfaction often occur as manifestations of a mood-related disorder, they may also be a consequence of pharmacologic treatment. In particular, some evidence suggests that SSRIs can cause such untoward sexual experiences. Reliable estimates of the incidence and severity of untoward experiences involving sexual desire, performance, and satisfaction are difficult to obtain, however, in part because patients and physicians may be reluctant to discuss them. Accordingly, estimates of the incidence of untoward sexual experience and performance, cited in product labeling, are likely to underestimate their actual incidence. For example, in women (age 18 to 45) receiving fluoxetine for indications other than PMDD, decreased libido was seen at an incidence of 4% for fluoxetine compared with 1% for placebo. There have been spontaneous reports in women (age 18 to 45) taking fluoxetine for indications other than PMDD of orgasmic dysfunction, including anorgasmia.

There are no adequate and well-controlled studies examining sexual dysfunction with fluoxetine treatment. While it is difficult to know the precise risk of sexual dysfunction associated with the use of SSRIs, physicians should routinely inquire about such possible side effects.

6.2 Other Reactions

Following is a list of all treatment-emergent adverse reactions reported at anytime by females and males taking fluoxetine in all US clinical trials for conditions other than PMDD as of May 8, 1995 (10,782 patients) except (1) those listed in the body or footnotes of Tables 1 or 5 above or elsewhere in labeling; (2) those for which the COSTART terms were uninformative or misleading; (3) those adverse reactions for which a causal relationship to fluoxetine use was considered remote; (4) adverse reactions occurring in only 1 patient treated with fluoxetine and which did not have a substantial probability of being acutely life-threatening; and (5) adverse reactions that could only occur in males.

Adverse reactions are classified within body system categories using the following definitions: frequent adverse reactions are defined as those occurring on one or more occasions in at least 1/100 patients; infrequent adverse reactions are those occurring in 1/100 to 1/1,000 patients; rare adverse reactions are those occurring in less than 1/1,000 patients.

Body as a Whole — Frequent: chest pain and chills; Infrequent: face edema, intentional overdose, malaise, pelvic pain, suicide attempt; Rare: acute abdominal syndrome, hypothermia, intentional injury, photosensitivity reaction.

Cardiovascular System — Frequent: hypertension; Infrequent: angina pectoris, arrhythmia, congestive heart failure, hypotension, migraine, myocardial infarct, postural hypotension, syncope, vascular headache; Rare: bradycardia, cerebral embolism, cerebral ischemia, extrasystoles, heart block, pallor, peripheral vascular disorder, phlebitis, shock, thrombophlebitis, thrombosis, vasospasm, ventricular arrhythmia, ventricular extrasystoles, ventricular fibrillation.

Digestive System — Frequent: increased appetite; Infrequent: aphthous stomatitis, cholelithiasis, colitis, dysphagia, eructation, esophagitis, gastritis, gastroenteritis, glossitis, gum hemorrhage, hyperchlorhydria, increased salivation, liver function tests abnormal, melena, mouth ulceration, stomach ulcer, stomatitis, thirst; Rare: biliary pain, bloody diarrhea, cholecystitis, duodenal ulcer, enteritis, esophageal ulcer, fecal incontinence, hepatitis, intestinal obstruction, liver fatty deposit, pancreatitis, peptic ulcer, salivary gland enlargement, tongue edema.

Endocrine System — Infrequent: hypothyroidism; Rare: diabetic acidosis, diabetes mellitus.

Hemic and Lymphatic System — Infrequent: anemia, ecchymosis; Rare: blood dyscrasia, hypochromic anemia, leukopenia, lymphedema, lymphocytosis, petechia, purpura, thrombocythemia.

Metabolic and Nutritional — Infrequent: dehydration, generalized edema, gout, hypercholesteremia, hyperlipemia, hypokalemia, peripheral edema; Rare: alcohol intolerance, alkaline phosphatase increased, BUN increased, creatine phosphokinase increased, hyperkalemia, hyperuricemia, hypocalcemia, iron deficiency anemia, SGPT increased.

Musculoskeletal System — Infrequent: arthritis, bone pain, bursitis, leg cramps, tenosynovitis; Rare: arthrosis, chondrodystrophy, myasthenia, myopathy, myositis, osteomyelitis, osteoporosis, rheumatoid arthritis.

Nervous System — Frequent: amnesia, emotional lability, paresthesia, and sleep disorder; Infrequent: abnormal gait, acute brain syndrome, akathisia, apathy, ataxia, buccoglossal syndrome, CNS depression, CNS stimulation, depersonalization, euphoria, hostility, hyperkinesia, hypertonia, hypesthesia, incoordination, libido increased, myoclonus, neuralgia, neuropathy, neurosis, paranoid reaction, personality disorder^1, psychosis, vertigo; Rare: abnormal electroencephalogram, antisocial reaction, circumoral paresthesia, delusions, dysarthria, dystonia, extrapyramidal syndrome, foot drop, hyperesthesia, neuritis, paralysis, reflexes decreased, stupor.

Respiratory System — Infrequent: asthma, epistaxis, hiccup, hyperventilation; Rare: apnea, atelectasis, cough decreased, emphysema, hemoptysis, hypoventilation, hypoxia, larynx edema, lung edema, pneumothorax, stridor.

Skin and Appendages — Infrequent: acne, alopecia, contact dermatitis, eczema, maculopapular rash, skin discoloration, skin ulcer; Rare: furunculosis, herpes zoster, hirsutism, psoriasis, purpuric rash, seborrhea.

Special Senses — Frequent: ear pain, taste perversion, tinnitus; Infrequent: conjunctivitis, dry eyes, mydriasis, photophobia; Rare: blepharitis, deafness, diplopia, exophthalmos, glaucoma, hyperacusis, iritis, parosmia, scleritis, strabismus, taste loss, visual field defect.

Urogenital System — Infrequent: abortion^2, albuminuria, amenorrhea^2, anorgasmia, breast enlargement, breast pain, cystitis, dysuria, female lactation^2, fibrocystic breast^2, hematuria, leukorrhea^2, menorrhagia^2, metrorrhagia^2, nocturia, polyuria, urinary incontinence, urinary retention, urinary urgency, vaginal hemorrhage^2; Rare: breast engorgement, glycosuria, hypomenorrhea^2, kidney pain, oliguria, uterine hemorrhage^2, uterine fibroids enlarged^2.

^1Personality disorder is the COSTART term for designating non-aggressive objectionable behavior.

^2Adjusted for gender.

6.3 Postmarketing Experience

The following adverse reactions have been identified during post approval use of fluoxetine. Because these reactions are reported voluntarily from a population of uncertain size, it is difficult to reliably estimate their frequency or evaluate a causal relationship to drug exposure.

Voluntary reports of adverse reactions temporally associated with fluoxetine that have been received since market introduction and that may have no causal relationship with the drug include the following: aplastic anemia, atrial fibrillation^1, cataract, cerebrovascular accident^1, cholestatic jaundice, dyskinesia (including, for example, a case of buccal-lingual-masticatory syndrome with involuntary tongue protrusion reported to develop in a 77-year-old female after 5 weeks of fluoxetine therapy and which completely resolved over the next few months following drug discontinuation), eosinophilic pneumonia^1, epidermal necrolysis, erythema multiforme, erythema nodosum, exfoliative dermatitis, gynecomastia, heart arrest^1, hepatic failure/necrosis, hyperprolactinemia, hypoglycemia, immune-related hemolytic anemia, kidney failure, movement disorders developing in patients with risk factors including drugs associated with such reactions and worsening of pre-existing movement disorders, optic neuritis, pancreatitis^1, pancytopenia, pulmonary embolism, pulmonary hypertension, QT prolongation, Stevens-Johnson syndrome, thrombocytopenia^1, thrombocytopenic purpura, ventricular tachycardia (including torsades de pointes–type arrhythmias), vaginal bleeding, and violent behaviors^1, drug reaction with eosinophilia and systemic symptoms (DRESS), and anosmia, hyposmia.

^1These terms represent serious adverse reactions, but do not meet the definition for adverse drug reactions. They are included here because of their seriousness.

7 DRUG INTERACTIONS

The potential for interaction by a variety of mechanisms (for example, pharmacodynamic, pharmacokinetic drug inhibition or enhancement, etc.) is a possibility.

7.1 Monoamine Oxidase Inhibitors (MAOI)

Concomitant use of fluoxetine tablets in patients taking MAOIs is contraindicated. There have been reports of serious, sometimes fatal, reactions (including hyperthermia, rigidity, myoclonus, autonomic instability with possible rapid fluctuations of vital signs, and mental status changes that include extreme agitation progressing to delirium and coma) in patients receiving fluoxetine in combination with a monoamine oxidase inhibitor (MAOI), and in patients who have recently discontinued fluoxetine and are then started on an MAOI. Some cases presented with features resembling neuroleptic malignant syndrome. Therefore, fluoxetine, including fluoxetine tablet, should not be used in combination with an MAOI, or within a minimum of 14 days of discontinuing therapy with an MAOI [see Contraindications (4)]. Since fluoxetine and its major metabolite have very long elimination half-lives, at least 5 weeks (perhaps longer, especially if fluoxetine has been prescribed chronically and/or at higher doses) should be allowed after stopping fluoxetine before starting an MAOI [see Dosage and Administration (2.4 and 2.5), Contraindications (4.1), Warnings and Precautions (5.2), and Clinical Pharmacology (12.3)].

7.2 CNS Acting Drugs

Caution is advised if the concomitant administration of fluoxetine, including fluoxetine tablet, and other CNS acting drugs is required. In evaluating individual cases, consideration should be given to using lower initial doses of the concomitantly administered drugs, using conservative titration schedules, and monitoring of clinical status [see Clinical Pharmacology (12.3)].

7.3 Serotonergic Drugs

Based on the mechanism of action of SNRIs and SSRIs, including fluoxetine hydrochloride, and the potential for serotonin syndrome, caution is advised when fluoxetine hydrochloride is coadministered with other drugs that may affect the serotonergic neurotransmitter systems, such as triptans, linezolid (an antibiotic which is a reversible non-selective MAOI), lithium, tramadol, amphetamines, or St. John's Wort [see Warnings and Precautions (5.2)]. The concomitant use of fluoxetine hydrochloride with SNRIs, SSRIs, or tryptophan is not recommended [see Dosage and Administration (2.4 and 2.5), Contraindications (4.1), Warnings and Precautions (5.2), and Drug Interactions (7.4), (7.5)].

7.4 Triptans

There have been rare postmarketing reports of serotonin syndrome with use of an SSRI and a triptan. If concomitant treatment of fluoxetine hydrochloride with a triptan is clinically warranted, careful observation of the patient is advised, particularly during treatment initiation and dose increases [see Warnings and Precautions (5.2) and Drug Interactions (7.3)].

7.5 Tryptophan

Five patients receiving fluoxetine in combination with tryptophan experienced adverse reactions, including agitation, restlessness, and gastrointestinal distress. The concomitant use with tryptophan is not recommended [see Warnings and Precautions (5.2) and Drug Interactions (7.3)].

7.6 Drugs that Interfere with Hemostasis (for example, NSAIDS, Aspirin, Warfarin)

Serotonin release by platelets plays an important role in hemostasis. Epidemiological studies of the case-control and cohort design that have demonstrated an association between use of psychotropic drugs that interfere with serotonin reuptake and the occurrence of upper gastrointestinal bleeding have also shown that concurrent use of an NSAID or aspirin may potentiate this risk of bleeding. Altered anticoagulant effects, including increased bleeding, have been reported when SNRIs or SSRIs are coadministered with warfarin. Patients receiving warfarin therapy should be carefully monitored when fluoxetine is initiated or discontinued [see Warnings and Precautions (5.7)].

7.7 Electroconvulsive Therapy (ECT)

There are no clinical studies establishing the benefit of the combined use of ECT and fluoxetine. There have been rare reports of prolonged seizures in patients on fluoxetine receiving ECT treatment.

7.8 Potential for Other Drugs to affect Fluoxetine hydrochloride

Drugs Tightly Bound to Plasma Proteins — Because fluoxetine is tightly bound to plasma proteins, adverse effects may result from displacement of protein-bound fluoxetine by other tightly bound drugs [see Clinical Pharmacology (12.3)].

7.9 Potential for Fluoxetine hydrochloride to affect Other Drugs

Pimozide — Concomitant use of fluoxetine hydrochloride in patients taking pimozide is contraindicated. Clinical studies of pimozide with other antidepressants demonstrate an increase in drug interaction or QTc prolongation. While a specific study with pimozide and fluoxetine has not been conducted, the potential for drug interactions or QTc prolongation warrants restricting the concurrent use of pimozide and fluoxetine [see Contraindications (4)].

Thioridazine — Concomitant use of fluoxetine hydrochloride in patients taking thioridazine is contraindicated. Thioridazine should not be administered with fluoxetine or within a minimum of 5 weeks after fluoxetine has been discontinued [see Contraindications (4)].

In a study of 19 healthy male subjects, which included 6 slow and 13 rapid hydroxylators of debrisoquin, a single 25 mg oral dose of thioridazine produced a 2.4-fold higher C max and a 4.5-fold higher AUC for thioridazine in the slow hydroxylators compared with the rapid hydroxylators. The rate of debrisoquin hydroxylation is felt to depend on the level of CYP2D6 isozyme activity. Thus, this study suggests that drugs which inhibit CYP2D6, such as certain SSRIs, including fluoxetine, will produce elevated plasma levels of thioridazine.

Thioridazine administration produces a dose-related prolongation of the QTc interval, which is associated with serious ventricular arrhythmias, such as torsades de pointes-type arrhythmias, and sudden death. This risk is expected to increase with fluoxetine-induced inhibition of thioridazine metabolism.

Drugs Metabolized by CYP2D6 — Fluoxetine inhibits the activity of CYP2D6, and may make individuals with normal CYP2D6 metabolic activity resemble a poor metabolizer. Coadministration of fluoxetine with other drugs that are metabolized by CYP2D6, including certain antidepressants (for example, tricyclic antidepressants (TCAs)), antipsychotics (for example, phenothiazines and most atypicals), and antiarrhythmics (for example, propafenone, flecainide, and others) should be approached with caution. Therapy with medications that are predominantly metabolized by the CYP2D6 system and that have a relatively narrow therapeutic index (see list below) should be initiated at the low end of the dose range if a patient is receiving fluoxetine concurrently or has taken it in the previous 5 weeks. Thus, his/her dosing requirements resemble those of poor metabolizers. If fluoxetine is added to the treatment regimen of a patient already receiving a drug metabolized by CYP2D6, the need for decreased dose of the original medication should be considered. Drugs with a narrow therapeutic index represent the greatest concern (for example, flecainide, propafenone, vinblastine, and TCAs). Due to the risk of serious ventricular arrhythmias and sudden death potentially associated with elevated plasma levels of thioridazine, thioridazine should not be administered with fluoxetine or within a minimum of 5 weeks after fluoxetine has been discontinued [see Contraindications (4)].

Tricyclic Antidepressants (TCAs) — In 2 studies, previously stable plasma levels of imipramine and desipramine have increased greater than 2- to 10-fold when fluoxetine has been administered in combination. This influence may persist for 3 weeks or longer after fluoxetine is discontinued. Thus, the dose of TCAs may need to be reduced and plasma TCA concentrations may need to be monitored temporarily when fluoxetine is coadministered or has been recently discontinued [see Clinical Pharmacology (12.3)].

Benzodiazapines — The half-life of concurrently administered diazepam may be prolonged in some patients [see Clinical Pharmacology (12.3)]. Coadministration of alprazolam and fluoxetine has resulted in increased alprazolam plasma concentrations and in further psychomotor performance decrement due to increased alprazolam levels.

Antipsychotics — Some clinical data suggests a possible pharmacodynamic and/or pharmacokinetic interaction between SSRIs and antipsychotics. Elevation of blood levels of haloperidol and clozapine has been observed in patients receiving concomitant fluoxetine [see Contraindications (4)].

Anticonvulsants — Patients on stable doses of phenytoin and carbamazepine have developed elevated plasma anticonvulsant concentrations and clinical anticonvulsant toxicity following initiation of concomitant fluoxetine treatment.

Lithium — There have been reports of both increased and decreased lithium levels when lithium was used concomitantly with fluoxetine. Cases of lithium toxicity and increased serotonergic effects have been reported. Lithium levels should be monitored when these drugs are administered concomitantly.

Drugs Tightly Bound to Plasma Proteins — Because fluoxetine is tightly bound to plasma proteins, the administration of fluoxetine to a patient taking another drug that is tightly bound to protein (for example, warfarin, digitoxin) may cause a shift in plasma concentrations potentially resulting in an adverse effect [see Clinical Pharmacology (12.3)].

Drugs Metabolized by CYP3A4 — In an in vivo interaction study involving coadministration of fluoxetine with single doses of terfenadine (a CYP3A4 substrate), no increase in plasma terfenadine concentrations occurred with concomitant fluoxetine.

Additionally, in vitro studies have shown ketoconazole, a potent inhibitor of CYP3A4 activity, to be at least 100 times more potent than fluoxetine or norfluoxetine as an inhibitor of the metabolism of several substrates for this enzyme, including astemizole, cisapride, and midazolam. These data indicate that fluoxetine's extent of inhibition of CYP3A4 activity is not likely to be of clinical significance.

8 USE IN SPECIFIC POPULATIONS

8.1 Pregnancy

Pregnancy Category C — It should be noted that the diagnosis of PMDD does exist during pregnancy. Fluoxetine should be used during pregnancy only if the potential benefit justifies the potential risk to the fetus. All pregnancies have a background risk of birth defects, loss, or other adverse outcome regardless of drug exposure. .

Treatment of Pregnant Women during the First Trimester — There are no adequate and well-controlled clinical studies on the use of fluoxetine in pregnant women. Results of a number of published epidemiological studies assessing the risk of fluoxetine exposure during the first trimester of pregnancy have demonstrated inconsistent results. More than 10 cohort studies and case-control studies failed to demonstrate an increased risk for congenital malformations overall. However, one prospective cohort study conducted by the European Network of Teratology Information Services reported an increased risk of cardiovascular malformations in infants born to women (N = 253) exposed to fluoxetine during the first trimester of pregnancy compared to infants of women (N = 1,359) who were not exposed to fluoxetine. There was no specific pattern of cardiovascular malformations. Overall, however, a causal relationship has not been established.

Non-teratogenic Effects — Based on data from published observational studies, exposure to SSRIs, particularly in the month before delivery, has been associated with a less than 2-fold increase in the risk of postpartum hemorrhage [see Warnings and Precautions (5.7) and Clinical Considerations]. Neonates exposed to fluoxetine and other SSRIs or serotonin and norepinephrine reuptake inhibitors (SNRIs), late in the third trimester have developed complications requiring prolonged hospitalization, respiratory support, and tube feeding. Such complications can arise immediately upon delivery. Reported clinical findings have included respiratory distress, cyanosis, apnea, seizures, temperature instability, feeding difficulty, vomiting, hypoglycemia, hypotonia, hypertonia, hyperreflexia, tremor, jitteriness, irritability, and constant crying. These features are consistent with either a direct toxic effect of SSRIs and SNRIs or, possibly, a drug discontinuation syndrome. It should be noted that, in some cases, the clinical picture is consistent with serotonin syndrome [see Warnings and Precautions (5.2)].

Maternal Adverse Reactions — Use of fluoxetine tablets in the month before delivery may be associated with an increased risk of postpartum hemorrhage [see Warnings and Precautions (5.7)].

Infants exposed to SSRIs in pregnancy may have an increased risk for persistent pulmonary hypertension of the newborn (PPHN). PPHN occurs in 1 to 2 per 1,000 live births in the general population and is associated with substantial neonatal morbidity and mortality. Several recent epidemiological studies suggest a positive statistical association between SSRI use (including fluoxetine) in pregnancy and PPHN. Other studies do not show a significant statistical association.

Physicians should also note the results of a prospective longitudinal study of 201 pregnant women with a history of major depression, who were either on antidepressants or had received antidepressants less than 12 weeks prior to their last menstrual period, and were in remission. Women who discontinued antidepressant medication during pregnancy showed a significant increase in relapse of their major depression compared to those women who remained on antidepressant medication throughout pregnancy.

When treating a pregnant woman with fluoxetine the physician should carefully consider both the potential risks of taking an SSRI, along with the established benefits of treating depression with an antidepressant. The decision can only be made on a case by case basis .

Animal Data — In embryo-fetal development studies in rats and rabbits, there was no evidence of teratogenicity following administration of fluoxetine at doses up to 12.5 and 15 mg/kg/day, respectively (1.5 and 3.6 times, respectively, the maximum recommended human dose (MRHD) of 80 mg on a mg/m^2 basis) throughout organogenesis. However, in rat reproduction studies, an increase in stillborn pups, a decrease in pup weight, and an increase in pup deaths during the first 7 days postpartum occurred following maternal exposure to 12 mg/kg/day (1.5 times the MRHD on a mg/m^2 basis) during gestation or 7.5 mg/kg/day (0.9 times the MRHD on a mg/m^2 basis) during gestation and lactation. There was no evidence of developmental neurotoxicity in the surviving offspring of rats treated with 12 mg/kg/day during gestation. The no-effect dose for rat pup mortality was 5 mg/kg/day (0.6 times the MRHD on a mg/m^2 basis).

8.2 Labor and Delivery

The effect of fluoxetine on labor and delivery in humans is unknown. However, because fluoxetine crosses the placenta and because of the possibility that fluoxetine may have adverse effects on the newborn, fluoxetine should be used during labor and delivery only if the potential benefit justifies the potential risk to the fetus.

8.3 Nursing Mothers

Because fluoxetine is excreted in human milk, nursing while on fluoxetine tablet is not recommended. In one breast-milk sample, the concentration of fluoxetine plus norfluoxetine was 70.4 ng/mL. The concentration in the mother's plasma was 295.0 ng/mL. No adverse effects on the infant were reported. In another case, an infant nursed by a mother on fluoxetine developed crying, sleep disturbance, vomiting, and watery stools. The infant's plasma drug levels were 340 ng/mL of fluoxetine and 208 ng/mL of norfluoxetine on the second day of feeding.

8.4 Pediatric Use

Safety and effectiveness of fluoxetine tablets in the pediatric population have not been established [see Boxed Warning and Warnings and Precautions (5.1)]. When considering the use of fluoxetine tablets in a child or adolescent, the potential risks must be balanced with the clinical need. Significant toxicity, including myotoxicity, long-term neurobehavioral and reproductive toxicity, and impaired bone development, has been observed following exposure of juvenile animals to fluoxetine. Some of these effects occurred at clinically relevant exposures.

As with other SSRIs, decreased weight gain has been observed in association with the use of fluoxetine in children and adolescent patients. After 19 weeks of treatment in a clinical trial, pediatric subjects treated with fluoxetine gained an average of 1.1 cm less in height and 1.1 kg less in weight than subjects treated with placebo. In addition, fluoxetine treatment was associated with a decrease in alkaline phosphatase levels. The safety of fluoxetine treatment for pediatric patients has not been systematically assessed for chronic treatment longer than several months in duration. In particular, there are no studies that directly evaluate the longer-term effects of fluoxetine on the growth, development and maturation of children and adolescent patients. Therefore, height and weight should be monitored periodically in pediatric patients receiving fluoxetine [see Warnings and Precautions (5.6)].

In a study in which fluoxetine (3, 10, or 30 mg/kg) was orally administered to young rats from weaning (Postnatal Day 21) through adulthood (Day 90), male and female sexual development was delayed at all doses, and growth (body weight gain, femur length) was decreased during the dosing period in animals receiving the highest dose. At the end of the treatment period, serum levels of creatine kinase (marker of muscle damage) were increased at the intermediate and high doses, and abnormal muscle and reproductive organ histopathology (skeletal muscle degeneration and necrosis, testicular degeneration and necrosis, epididymal vacuolation and hypospermia) was observed at the high dose. When animals were evaluated after a recovery period (up to 11 weeks after cessation of dosing), neurobehavioral abnormalities (decreased reactivity at all doses and learning deficit at the high dose) and reproductive functional impairment (decreased mating at all doses and impaired fertility at the high dose) were seen; in addition, testicular and epididymal microscopic lesions and decreased sperm concentrations were found in the high dose group, indicating that the reproductive organ effects seen at the end of treatment were irreversible. The reversibility of fluoxetine-induced muscle damage was not assessed. Adverse effects similar to those observed in rats treated with fluoxetine during the juvenile period have not been reported after administration of fluoxetine to adult animals. Plasma exposures (AUC) to fluoxetine in juvenile rats receiving the low, intermediate, and high dose in this study were approximately 0.1 to 0.2, 1 to 2, and 5 to 10 times, respectively, the average exposure in pediatric patients receiving the maximum recommended dose (MRD) of 20 mg/day. Rat exposures to the major metabolite, norfluoxetine, were approximately 0.3 to 0.8, 1 to 8, and 3 to 20 times, respectively, pediatric exposure at the MRD.

A specific effect of fluoxetine on bone development has been reported in mice treated with fluoxetine during the juvenile period. When mice were treated with fluoxetine (5 or 20 mg/kg, intraperitoneal) for 4 weeks starting at 4 weeks of age, bone formation was reduced resulting in decreased bone mineral content and density. These doses did not affect overall growth (body weight gain or femoral length). The doses administered to juvenile mice in this study are approximately 0.5 and 2 times the MRD for pediatric patients on a body surface area (mg/m^2) basis.

In another mouse study, administration of fluoxetine (10 mg/kg intraperitoneal) during early postnatal development (Postnatal Days 4 to 21) produced abnormal emotional behaviors (decreased exploratory behavior in elevated plus-maze, increase shock avoidance latency) in adulthood (12 weeks of age). The dose used in this study is approximately equal to the pediatric MRD on a mg/m^2 basis. Because of the early dosing period in this study, the significance of these findings to the approved pediatric use in humans is uncertain.

8.5 Geriatric Use

The diagnosis of PMDD is not applicable to postmenopausal women.

8.6 Hepatic Impairment

In subjects with cirrhosis of the liver, the clearances of fluoxetine and its active metabolite, norfluoxetine, were decreased, thus increasing the elimination half-lives of these substances. A lower or less frequent dose of fluoxetine should be used in patients with cirrhosis. Caution is advised when using fluoxetine tablet in patients with diseases or conditions that could affect its metabolism [see Dosage and Administration (2.3) and Clinical Pharmacology (12.3)].

9 DRUG ABUSE AND DEPENDENCE

9.3 Dependence

Fluoxetine has not been systematically studied, in animals or humans, for its potential for abuse, tolerance, or physical dependence. While the pre-marketing clinical experience with fluoxetine did not reveal any tendency for a withdrawal syndrome or any drug seeking behavior, these observations were not systematic and it is not possible to predict on the basis of this limited experience the extent to which a CNS active drug will be misused, diverted, and/or abused once marketed. Consequently, physicians should carefully evaluate patients for history of drug abuse and follow such patients closely, observing them for signs of misuse or abuse of fluoxetine tablet (for example, development of tolerance, incrementation of dose, drug-seeking behavior).

10 OVERDOSAGE

The following have been reported with fluoxetine tablet overdosage:
• Seizures, which may be delayed, and altered mental status including coma.
• Cardiovascular toxicity, which may be delayed, including QRS and QTc interval prolongation, wide complex tachyarrhythmias, torsade de pointes, and cardiac arrest. Hypertension most commonly seen, but rarely can see hypotension alone or with co-ingestants including alcohol.
• Serotonin syndrome (patients with a multiple drug overdosage with other proserotonergic drugs may have a higher risk).

Gastrointestinal decontamination with activated charcoal should be considered in patients who present early after a fluoxetine overdose.

Consider contacting a poison center (1-800-221-2222) or a medical toxicologist for overdosage management recommendations.

11 DESCRIPTION

Fluoxetine tablets, USP are a selective serotonin reuptake inhibitor (SSRI) for oral administration. It is designated (±)-N-methyl-3-phenyl-3-[(α,α,α-trifluoro- p-tolyl)oxy]propylamine hydrochloride and has the empirical formula of C17H18F3NO•HCl. Its molecular weight is 345.79. The structural formula is:

Fluoxetine hydrochloride, USP is a white to off-white crystalline solid with a solubility of 14 mg/mL in water.

Each Fluoxetine tablets, USP contains fluoxetine hydrochloride equivalent to 10 mg or 20 mg of fluoxetine. Each tablet also contains colloidal silicon dioxide, croscarmellose sodium, D&C yellow no. 10 lake, FD&C yellow no. 6 lake, magnesium stearate, microcrystalline cellulose, and povidone.

12 CLINICAL PHARMACOLOGY

12.1 Mechanisam of Action

Although the exact mechanism of fluoxetine hydrochloride is unknown, it is presumed to be linked to its inhibition of CNS neuronal uptake of serotonin.

12.2 Pharmacodynamics

Studies at clinically relevant doses in humans have demonstrated that fluoxetine blocks the uptake of serotonin into human platelets. Studies in animals also suggest that fluoxetine is a much more potent uptake inhibitor of serotonin than of norepinephrine.

Antagonism of muscarinic, histaminergic, and α1-adrenergic receptors has been hypothesized to be associated with various anticholinergic, sedative, and cardiovascular effects of classical tricyclic antidepressant (TCA) drugs. Fluoxetine binds to these and other membrane receptors from brain tissue much less potently in vitro than do the tricyclic drugs.

Enantiomers — Fluoxetine is a racemic mixture (50/50) of R-fluoxetine and S-fluoxetine enantiomers. In animal models, both enantiomers are specific and potent serotonin uptake inhibitors with essentially equivalent pharmacologic activity. The S-fluoxetine enantiomer is eliminated more slowly and is the predominant enantiomer present in plasma at steady state.

12.3 Pharmacokinetics

Systemic Bioavailability/Absorption —Mean plasma fluoxetine concentrations following single-dose administration of fluoxetine hydrochloride 20 mg tablets are shown in Figure 1; fluoxetine and norfluoxetine pharmacokinetic parameters are shown in Table 7.

Figure 1. Mean (± SD) Plasma Fluoxetine Concentrations Following Single- Dose Administration of Fluoxetine Hydrochloride 20 mg Tablets to Healthy Female Volunteers (n = 23)

Table 7. Summary of Mean Pharmacokinetic Parameters Following Single-Dose Administration of Fluoxetine 20 mg Tablets to Healthy Female Volunteers (n = 23) (Cmax and AUC(0-t): shown as Mean (% Coefficient of Variation); Tmax and T1/2: shown as median (range))
Dose | Analyte | Cmax (ng/mL) | Tmax (hour) | AUC(0-T) (ng.h/mL) | T½a (hour)
Fluoxetine tablet 20 mg | Fluoxetine | 13.2 (22) | 8.0 (2.0 to 10.0) | 722.4 (138) | 26.5 (15.7 to 310.0)
Fluoxetine tablet 20 mg | Norfluoxetine | 9.7 (37) | 48.0 (11.0 to 144.0) | 2114.3 (41) | 110.4 (66.8 to 308.0)
a) 3 subjects had longer fluoxetine elimination half-life values ranging from 100 to 300 hours; see Clinical issues relating to metabolism/elimination for more information on "poor metabolizers"

Food does not appear to affect the systemic bioavailability of fluoxetine, although it may delay its absorption by 1 to 2 hours, which is probably not clinically significant. Thus, fluoxetine may be administered with or without food.

Protein Binding — Over the concentration range from 200 to 1,000 ng/mL, approximately 94.5% of fluoxetine is bound in vitro to human serum proteins, including albumin and α1-glycoprotein. The interaction between fluoxetine and other highly protein-bound drugs has not been fully evaluated, but may be important [see Drug Interactions (7.8 and 7.9)].

Metabolism — Fluoxetine is extensively metabolized in the liver to norfluoxetine and a number of other unidentified metabolites. The only identified active metabolite, norfluoxetine, is formed by demethylation of fluoxetine. In animal models, S-norfluoxetine is a potent and selective inhibitor of serotonin uptake and has activity essentially equivalent to R- or S-fluoxetine. R-norfluoxetine is significantly less potent than the parent drug in the inhibition of serotonin uptake.

Variability in Metabolism — A subset (about 7%) of the population has reduced activity of the drug metabolizing enzyme cytochrome P450 2D6 (CYP2D6). Such individuals are referred to as "poor metabolizers" of drugs such as debrisoquin, dextromethorphan, and the TCAs. In a study involving labeled and unlabeled enantiomers administered as a racemate, these individuals metabolized S-fluoxetine at a slower rate and thus achieved higher concentrations of S-fluoxetine. Consequently, concentrations of S-norfluoxetine at steady state were lower. The metabolism of R-fluoxetine in these poor metabolizers appears normal. When compared with normal metabolizers, the total sum at steady state of the plasma concentrations of the 4 active enantiomers was not significantly greater among poor metabolizers. Thus, the net pharmacodynamic activities were essentially the same. Alternative, nonsaturable pathways (non-2D6) also contribute to the metabolism of fluoxetine. This explains how fluoxetine achieves a steady-state concentration rather than increasing without limit.

Because fluoxetine's metabolism, like that of a number of other compounds including TCAs and other selective serotonin reuptake inhibitors (SSRIs), involves the CYP2D6 system, concomitant therapy with drugs also metabolized by this enzyme system (such as the TCAs) may lead to drug interactions [see Drug Interactions (7.9)].

Excretion — The primary route of elimination appears to be hepatic metabolism to inactive metabolites excreted by the kidney.

Accumulation and Slow Elimination — The relatively slow elimination of fluoxetine (elimination half-life of 1 to 3 days after acute administration and 4 to 6 days after chronic administration) and its active metabolite, norfluoxetine (elimination half-life of 4 to 16 days after acute and chronic administration), leads to significant accumulation of these active species in chronic use and delayed attainment of steady state, even when a fixed dose is used [see Warnings and Precautions (5.12)]. After 30 days of dosing at 40 mg/day, plasma concentrations of fluoxetine in the range of 91 to 302 ng/mL and norfluoxetine in the range of 72 to 258 ng/mL have been observed. Plasma concentrations of fluoxetine were higher than those predicted by single-dose studies, because fluoxetine's metabolism is not proportional to dose. Norfluoxetine, however, appears to have linear pharmacokinetics. Its mean terminal half-life after a single dose was 8.6 days and after multiple dosing was 9.3 days. Steady-state levels after prolonged dosing are similar to levels seen at 4 to 5 weeks.

The long elimination half-lives of fluoxetine and norfluoxetine assure that, even when dosing is stopped, active drug substance will persist in the body for weeks (primarily depending on individual patient characteristics, previous dosing regimen, and length of previous therapy at discontinuation). This is of potential consequence when drug discontinuation is required or when drugs are prescribed that might interact with fluoxetine and norfluoxetine following the discontinuation of fluoxetine tablet.

Hepatic Impairment — As might be predicted from its primary site of metabolism, liver impairment can affect the elimination of fluoxetine. The elimination half-life of fluoxetine was prolonged in a study of cirrhotic patients, with a mean of 7.6 days compared with the range of 2 to 3 days seen in subjects without liver disease; norfluoxetine elimination was also delayed, with a mean duration of 12 days for cirrhotic patients compared with the range of 7 to 9 days in normal subjects. This suggests that the use of fluoxetine in patients with liver disease must be approached with caution. If fluoxetine is administered to patients with liver disease, a lower or less frequent dose should be used [see Dosage and Administration (2.3), Use in Specific Populations (8.6)].

Renal Impairment — In depressed patients on dialysis (N = 12), fluoxetine administered as 20 mg once daily for 2 months produced steady-state fluoxetine and norfluoxetine plasma concentrations comparable with those seen in patients with normal renal function. While the possibility exists that renally excreted metabolites of fluoxetine may accumulate to higher levels in patients with severe renal dysfunction, use of a lower or less frequent dose is not routinely necessary in renally impaired patients.

13 NONCLINICAL TOXICOLOGY

13.1 Carcinogenesis, Mutagenesis, Impairment of Fertility

Carcinogenicity — The dietary administration of fluoxetine to rats and mice for 2 years at doses of up to 10 and 12 mg/kg/day, respectively [approximately 1.2 and 0.7 times, respectively, the maximum recommended human dose (MRHD) of 80 mg on a mg/m^2 basis], produced no evidence of carcinogenicity.

Mutagenicity — Fluoxetine and norfluoxetine have been shown to have no genotoxic effects based on the following assays: bacterial mutation assay, DNA repair assay in cultured rat hepatocytes, mouse lymphoma assay, and in vivo sister chromatid exchange assay in Chinese hamster bone marrow cells.

Impairment of Fertility — Two fertility studies conducted in adult rats at doses of up to 7.5 and 12.5 mg/kg/day (approximately 0.9 and 1.5 times the MRHD on a mg/m^2 basis) indicated that fluoxetine had no adverse effects on fertility. However, adverse effects on fertility were seen when juvenile rats were treated with fluoxetine [see Use in Specific Populations (8.4)].

13.2 Animal Toxicology and/or Pharmacology

Phospholipids are increased in some tissues of mice, rats, and dogs given fluoxetine chronically. This effect is reversible after cessation of fluoxetine treatment. Phospholipid accumulation in animals has been observed with many cationic amphiphilic drugs, including fenfluramine, imipramine, and ranitidine. The significance of this effect in humans is unknown.

14 CLINICAL STUDIES

14.1 Premenstrual Dysphoric Disorder (PMDD)

The effectiveness of fluoxetine hydrochloride for the treatment of PMDD was established in 3 placebo-controlled trials (1 intermittent and 2 continuous dosing). In an intermittent dosing trial described below, patients met Diagnostic and Statistical Manual-4th edition (DSM-IV) criteria for PMDD. In the continuous dosing trials described below, patients met Diagnostic and Statistical Manual-3rd edition revised (DSM-IIIR) criteria for Late Luteal Phase Dysphoric Disorder (LLPDD), the clinical entity now referred to as PMDD in the DSM-IV. Patients on oral contraceptives were excluded from these trials; therefore, the efficacy of fluoxetine in combination with oral contraceptives for the treatment of PMDD is unknown.

In an intermittent dosing double-blind, parallel group study of 3 months duration, patients (N = 260 randomized) were treated with fluoxetine 10 mg/day, fluoxetine 20 mg/day, or placebo. Fluoxetine or placebo was started 14 days prior to the anticipated onset of menstruation and was continued through the first full day of menses. Efficacy was assessed with the Daily Record of Severity of Problems (DRSP), a patient-rated instrument that mirrors the diagnostic criteria for PMDD as identified in the DSM-IV, and includes assessments for mood, physical symptoms, and other symptoms. Fluoxetine 20 mg/day was shown to be significantly more effective than placebo as measured by the DRSP total score. Fluoxetine 10 mg/day was not shown to be significantly more effective than placebo on this outcome. The average DRSP total score decreased 38% on fluoxetine 20 mg/day, 35% on fluoxetine 10 mg/day, and 30% on placebo.

In the first continuous dosing double-blind, parallel group study of 6 months duration involving N = 320 patients, fixed doses of fluoxetine 20 and 60 mg/day given daily throughout the menstrual cycle were shown to be significantly more effective than placebo as measured by a Visual Analogue Scale (VAS) total score (including mood and physical symptoms). The average total VAS score decreased 7% on placebo treatment, 36% on 20 mg, and 39% on 60 mg fluoxetine. The difference between the 20 and 60 mg doses was not statistically significant. The following table shows the percentage of patients meeting criteria for either moderate or marked improvement on the VAS total score:

Table 8: Percentage of Patients Moderately and Markedly Improved (greater than 50% and 75% reduction, respectively, from baseline Luteal Phase VAS total score)
Improvement | N | Placebo | N | Fluoxetine 20 mg | N | Fluoxetine 60 mg
Moderate | 94 | 11% | 95 | 37% | 85 | 38%
Marked | 94 | 4% | 95 | 6% | 85 | 18%

In a second continuous dosing double-blind, cross-over study, patients (N = 19) were treated with fluoxetine 20 to 60 mg/day (mean dose = 27 mg/day) and placebo daily throughout the menstrual cycle for a period of 3 months each. Fluoxetine was significantly more effective than placebo as measured by within cycle follicular to luteal phase changes in the VAS total score (mood, physical, and social impairment symptoms). The average VAS total score (follicular to luteal phase increase) was 3.8 times higher during placebo treatment than what was observed during fluoxetine treatment.

In another continuous dosing double-blind, parallel group study, patients with LLPDD (N = 42) were treated daily with fluoxetine 20 mg/day, bupropion 300 mg/day, or placebo for 2 months. Neither fluoxetine nor bupropion was shown to be superior to placebo on the primary endpoint, that is, response rate [defined as a rating of 1 (very much improved) or 2 (much improved) on the CGI], possibly due to sample size.

16 HOW SUPPLIED/STORAGE AND HANDLING

16.1 How Supplied

Fluoxetine tablets, USP are available in 10 mg and 20 mg strengths.

10 mg - Light cream to cream colored, flat round, uncoated tablets with beveled edges, debossed with "43" on one side and plain on other side.

Bottles of 30 NDC 13668-443-30

Bottles of 100 NDC 13668-443-01

Bottles of 1,000 NDC 13668-443-10

100 Unit dose Tablets NDC 13668-443-74

28 Unit dose Tablets NDC 13668-443-91

20 mg - Light yellow to yellow colored, flat round, uncoated tablets with beveled edges, debossed with "73" on one side and plain on other side.

Bottles of 30 NDC 13668-473-30

Bottles of 100 NDC 13668-473-01

Bottles of 1,000 NDC 13668-473-10

100 Unit dose Tablets NDC 13668-473-74

28 Unit dose Tablets NDC 13668-473-91

16.2 Storage and Handling

Store at 20° to 25°C (68° to 77°F); excursions permitted to 15° to 30°C (59° to 86°F) [see USP Controlled Room Temperature].

17 PATIENT COUNSELING INFORMATION

See the FDA-approved Medication Guide.

17.1 General Information

Healthcare providers should instruct their patients to read the Medication Guide before starting therapy with fluoxetine tablet and to reread it each time the prescription is renewed.

Healthcare providers should inform patients, their families, and their caregivers about the benefits and risks associated with treatment with fluoxetine tablet and should counsel them in its appropriate use. Healthcare providers should instruct patients, their families, and their caregivers to read the Medication Guide and should assist them in understanding its contents. Patients should be given the opportunity to discuss the contents of the Medication Guide and to obtain answers to any questions they may have.

Patients should be advised of the following issues and asked to alert their healthcare provider if these occur while taking fluoxetine tablet.

17.2 Clinical Worsening and Suicide Risk

Patients, their families, and their caregivers should be encouraged to be alert to the emergence of anxiety, agitation, panic attacks, insomnia, irritability, hostility, aggressiveness, impulsivity, akathisia (psychomotor restlessness), hypomania, mania, other unusual changes in behavior, worsening of depression, and suicidal ideation, especially early during antidepressant treatment and when the dose is adjusted up or down. Families and caregivers of patients should be advised to look for the emergence of such symptoms on a day-to-day basis, since changes may be abrupt. Such symptoms should be reported to the patient's prescriber or health professional, especially if they are severe, abrupt in onset, or were not part of the patient's presenting symptoms. Symptoms such as these may be associated with an increased risk for suicidal thinking and behavior and indicate a need for very close monitoring and possibly changes in the medication [see Boxed Warning and Warnings and Precautions (5.1)].

17.3 Serotonin Syndrome

Patients should be cautioned about the risk of serotonin syndrome with the concomitant use of fluoxetine tablets and other serotonergic agents including triptans, tricyclic antidepressants, opioids, lithium, tryptophan, buspirone, amphetamines, and St. John's Wort [see Contraindications (4.1), Warnings and Precautions (5.2), and Drug Interactions (7.3)].

Patients should be advised of the signs and symptoms associated with serotonin syndrome that may include mental status changes (for example, agitation, hallucinations, delirium, and coma), autonomic instability (for example, tachycardia, labile blood pressure, dizziness, diaphoresis, flushing, hyperthermia), neuromuscular changes (for example, tremor, rigidity, myoclonus, hyperreflexia, incoordination), seizures, and/or gastrointestinal symptoms (for example, nausea, vomiting, diarrhea). Patients should be cautioned to seek medical care immediately if they experience these symptoms.

17.4 Allergic Reactions and Rash

Patients should be advised to notify their physician if they develop a rash or hives [see Warnings and Precautions (5.3)]. Patients should also be advised of the signs and symptoms associated with a severe allergic reaction, including swelling of the face, eyes, or mouth, or trouble breathing. Patients should be cautioned to seek medical care immediately if they experience these symptoms.

17.5 Abnormal Bleeding

Patients should be cautioned about the concomitant use of fluoxetine and NSAIDs, aspirin, warfarin, or other drugs that affect coagulation since combined use of psychotropic drugs that interfere with serotonin reuptake and these agents have been associated with an increased risk of bleeding [see Warnings and Precautions (5.7) and Drug Interactions (7.6)]. Patients should be advised to call their doctor if they experience any increased or unusual bruising or bleeding while taking fluoxetine tablet.

17.6 Angle-Closure Glaucoma

Patients should be advised that taking fluoxetine tablet can cause mild pupillary dilation, which in susceptible individuals, can lead to an episode of angle-closure glaucoma. Pre-existing glaucoma is almost always open-angle glaucoma because angle-closure glaucoma, when diagnosed, can be treated definitively with iridectomy. Open-angle glaucoma is not a risk factor for angle-closure glaucoma. Patients may wish to be examined to determine whether they are susceptible to angle-closure, and have a prophylactic procedure (e.g., iridectomy), if they are susceptible [See Warnings and Precautions (5.8)].

17.7 Hyponatremia

Patients should be advised that hyponatremia has been reported as a result of treatment with SNRIs and SSRIs, including fluoxetine tablet. Signs and symptoms of hyponatremia include headache, difficulty concentrating, memory impairment, confusion, weakness, and unsteadiness, which may lead to falls. More severe and/or acute cases have been associated with hallucination, syncope, seizure, coma, respiratory arrest, and death [see Warnings and Precautions (5.9)].

17.8 Potential for Cognitive and Motor Impairment

Fluoxetine hydrochloride may impair judgment, thinking, or motor skills. Patients should be advised to avoid driving a car or operating hazardous machinery until they are reasonably certain that their performance is not affected [see Warnings and Precautions (5.12)].

17.9 Use of Concomitant Medications

Patients should be advised to inform their physician if they are taking, or plan to take, any prescription medication, including Symbyax, Prozac, Prozac Weekly, or over-the-counter drugs, including herbal supplements or alcohol. Patients should also be advised to inform their physicians if they plan to discontinue any medications they are taking while on fluoxetine tablet.

17.10 Discontinuation of Treatment

Patients should be advised to take fluoxetine tablet exactly as prescribed, and to continue taking fluoxetine tablet as prescribed even after their symptoms improve. Patients should be advised that they should not alter their dosing regimen, or stop taking fluoxetine tablet without consulting their physician [see Warnings and Precautions (5.14)]. Patients should be advised to consult with their healthcare provider if their symptoms do not improve with fluoxetine tablet.

17.11 Use in Specific Populations

Pregnancy — Patients should be advised to notify their physician if they become pregnant or intend to become pregnant during therapy. Fluoxetine should be used during pregnancy only if the potential benefit justifies the potential risk to the fetus [see Use in Specific Populations (8.1)].

Nursing Mothers — Patients should be advised to notify their physician if they intend to breastfeed an infant during therapy. Because fluoxetine is excreted in human milk, nursing while taking fluoxetine tablet is not recommended [see Use in Specific Populations (8.3)].

17.12 Sexual Dysfunction

Advise patients that use of fluoxetine tablets may cause symptoms of sexual dysfunction in female patients. Inform patients that they should discuss any changes in sexual function and potential management strategies with their healthcare provider [see Warnings and Precautions (5.15)].

Manufactured by:

TORRENT PHARMACEUTICALS LTD., INDIA.

Manufactured for:

TORRENT PHARMA INC., Basking Ridge, NJ 07920

8093816 August 2023

Medication Guide

FLUOXETINE (Floa-OX-e-teen) TABLETS, USP

Read the Medication Guide that comes with fluoxetine tablets before you start taking it and each time you get a refill. There may be new information. This Medication Guide does not take the place of talking to your healthcare provider about your medical condition or treatment. Talk with your healthcare provider if there is something you do not understand or you want to learn more about.

Fluoxetine tablet is in a class of drugs called selective serotonin reuptake inhibitors (SSRIs), which are often used for the treatment of depression and anxiety disorders. Although fluoxetine tablets are not a treatment for depression, it contains fluoxetine hydrochloride, the same active ingredient in some antidepressants.

What is the most important information I should know about fluoxetine tablets?

Fluoxetine tablets and other antidepressant medicines may cause serious side effects including:

1. Suicidal thoughts or actions:

- Fluoxetine tablets and other antidepressant medicines may increase suicidal thoughts or actions in some children, teenagers, or young adults within the first few months of treatment or when the dose is changed.
- Depression or other serious mental illnesses are the most important causes of suicidal thoughts or actions.
- Watch for these changes and call your healthcare provider right away if you notice:

º New or sudden changes in mood, behavior, actions, thoughts, or feelings, especially if severe.

º Pay particular attention to such changes when fluoxetine tablets are started or when the dose is changed.

Keep all follow-up visits with your healthcare provider and call between visits if you are worried about symptoms.

Call your healthcare provider right away if you have any of the following symptoms, or call 911 if an emergency, especially if they are new, worse, or worry you:

- attempts to commit suicide
- acting on dangerous impulses
- acting aggressive or violent
- thoughts about suicide or dying
- new or worse depression
- new or worse anxiety or panic attacks
- feeling agitated, restless, angry or irritable
- trouble sleeping
- an increase in activity or talking more than what is normal for you
- other unusual changes in behavior or mood

Call your healthcare provider right away if you have any of the following symptoms, or call 911 if an emergency. Fluoxetine tablets may be associated with these serious side effects:

2. Serotonin Syndrome. This condition can be life-threatening and may include:

- agitation, hallucinations, coma or other changes in mental status
- coordination problems or muscle twitching (overactive reflexes)
- racing heartbeat, high or low blood pressure
- sweating or fever
- nausea, vomiting, or diarrhea
- muscle rigidity
- dizziness
- flushing
- tremor
- seizures

3. Severe allergic reactions:

- trouble breathing
- swelling of the face, tongue, eyes or mouth
- rash, itchy welts (hives) or blisters, alone or with fever or joint pain

4. Manic episodes:

- greatly increased energy
- severe trouble sleeping
- racing thoughts
- reckless behavior
- unusually grand ideas
- excessive happiness or irritability
- talking more or faster than usual

5. Seizures or convulsions

6. Changes in appetite or weight. Children and adolescents should have height and weight monitored during treatment.

7. Abnormal bleeding: Fluoxetine tablets and other antidepressant medicines may increase your risk of bleeding or bruising, especially if you take the blood thinner warfarin (Coumadin®, Jantoven®), a non-steroidal anti-inflammatory drug (NSAID's, like ibuprofen or naproxen), or aspirin.

8. Visual Problems

- eye pain
- changes in vision
- swelling or redness in or around the eye

Only some people are at risk for these problems. You may want to undergo an eye examination to see if you are at risk and receive preventative treatment if you are.

9. Low salt (sodium) levels in the blood. Elderly people may be at greater risk for this. Symptoms may include:

- headache
- weakness or feeling unsteady
- confusion, problems concentrating or thinking or memory problems

10. Sexual problems (dysfunction).Taking selective serotonin reuptake inhibitors (SSRIs), including fluoxetine tablets, may cause symptoms of sexual problems

Symptoms in females may include:

ο Decreased sex drive

ο Delayed or inability to have an orgasm

Talk to your healthcare provider if you develop any changes in your sexual function or if you have any questions or concerns about sexual problems during treatment with fluoxetine tablets. There may be treatments your healthcare provider can suggest.

Do not stop fluoxetine tablets without first talking to your healthcare provider. Stopping fluoxetine tablets too quickly may cause serious symptoms including:

- anxiety, irritability, high or low mood, feeling restless or changes in sleep habits
- headache, sweating, nausea, dizziness
- electric shock-like sensations, shaking, confusion

What are fluoxetine tablets?

Fluoxetine tablets are a prescription medicine used to treat premenstrual dysphoric disorder (PMDD).

It is not known if fluoxetine tablets are safe and effective in children.

Talk with your healthcare provider if you do not think that your condition is getting better with fluoxetine tablets treatment.

Who should not take fluoxetine tablets?

Do not take fluoxetine tablets if you:

- take a Monoamine Oxidase Inhibitor (MAOI). Ask your healthcare provider or pharmacist if you are not sure if you take an MAOI, including the antibiotic linezolid.

º Do not take an MAOI within 5 weeks of stopping fluoxetine tablets unless directed to do so by your healthcare provider.

º Do not start fluoxetine tablets if you stopped taking an MAOI in the last 2 weeks unless directed to do so by your healthcare provider.

Women who take fluoxetine tablets close in time to an MAOI may have serious or even life-threatening side effects. Get medical help right away if you have any of these symptoms:

- high fever
- uncontrolled muscle spasms
- stiff muscles
- rapid changes in heart rate or blood pressure
- confusion
- loss of consciousness (pass out)

- take Mellaril ® (thioridazine). Do not take Mellaril ® within 5 weeks of stopping fluoxetine tablets because this can cause serious heart rhythm problems or sudden death.
- take the antipsychotic medicine pimozide (Orap ®) because this can cause serious heart problems.

What should I tell my healthcare provider before taking fluoxetine tablets? Ask if you are not sure.

Before starting fluoxetine tablets, tell your healthcare provider if you:

- Are taking certain drugs or treatments such as:

º Triptans used to treat migraine headache

º Medicines used to treat mood, anxiety, psychotic or thought disorders, including tricyclics, lithium, buspirone, amphetamines, SSRIs, SNRIs, MAOIs or antipsychotics

º Tramadol, fentanyl, meperidine, methadone, or other opioids

º Over-the-counter supplements such as tryptophan or St. John's Wort

º Electroconvulsive therapy (ECT)

- have liver problems
- have kidney problems
- have heart problems
- have or had seizures or convulsions
- have bipolar disorder or mania
- have low sodium levels in your blood
- have a history of a stroke
- have high blood pressure
- have or had bleeding problems
- are pregnant or plan to become pregnant. It is not known if fluoxetine tablets will harm your unborn baby.
- are breastfeeding or plan to breastfeed. Some fluoxetine may pass into your breast milk. Talk to your healthcare provider about the best way to feed your baby while taking fluoxetine tablets.

Tell your healthcare provider about all the medicines that you take, including prescription and non-prescription medicines, vitamins, and herbal supplements. Fluoxetine tablets and some medicines may interact with each other, may not work as well, or may cause serious side effects.

Your healthcare provider or pharmacist can tell you if it is safe to take fluoxetine tablets with your other medicines. Do not start or stop any medicine while taking fluoxetine tablets without talking to your healthcare provider first.

If you take fluoxetine tablets, you should not take any other medicines that contain fluoxetine hydrochloride:

- Symbyax®
- Prozac®
- Prozac® WeeklyTM

How should I take fluoxetine tablets?

- Take fluoxetine tablets exactly as prescribed. Your healthcare provider may need to change the dose of fluoxetine tablets until it is the right dose for you.
- Talk to your healthcare provider if your symptoms do not get better.
- Fluoxetine tablets may be taken with or without food.
- If you take too much fluoxetine tablets, call your healthcare provider or go to the nearest hospital emergency room right away.

What should I avoid while taking fluoxetine tablets?

Fluoxetine tablets can cause sleepiness or may affect your ability to make decisions, think clearly, or react quickly. You should not drive, operate heavy machinery, or do other dangerous activities until you know how fluoxetine tablets affects you. Do not drink alcohol while using fluoxetine tablets.

What are the possible side effects of fluoxetine tablets?

Fluoxetine tablets may cause serious side effects, including:

- See "What is the most important information I should know about fluoxetine tablets?"
- Problems with blood sugar control. Women who have diabetes and take fluoxetine tablets may have problems with low blood sugar while taking fluoxetine tablets. High blood sugar can happen when fluoxetine tablets is stopped. Your healthcare provider may need to change the dose of your diabetes medicines when you start or stop taking fluoxetine tablets.
- Feeling anxious or trouble sleeping

The most common side effects of fluoxetine tablets include:

- headache
- weakness (asthenia)
- pain
- accidental injury
- infection
- flu symptoms
- nausea
- diarrhea
- trouble sleeping (insomnia)
- dizziness
- feeling anxious or nervous
- thinking differently
- sexual problems
- runny or stuffy nose (rhinitis)
- sore throat (pharyngitis)

Tell your healthcare provider if you have any side effect that bothers you or that does not go away. These are not all the possible side effects of fluoxetine tablets. For more information, ask your healthcare provider or pharmacist.

Call your doctor for medical advice about side effects. You may report side effects to FDA at 1-800-FDA-1088.

How should I store fluoxetine tablets?

- Store fluoxetine tablets at 20° to 25°C (68° to 77°F); excursions permitted to 15° to 30°C (59° to 86°F) [see USP Controlled Room Temperature].

Keep fluoxetine tablets and all medicines out of the reach of children.

General information about fluoxetine tablets

Medicines are sometimes prescribed for purposes other than those listed in a Medication Guide. Do not use fluoxetine tablets for a condition for which it was not prescribed. Do not give fluoxetine tablets to other people, even if they have the same condition. It may harm them.

This Medication Guide summarizes the most important information about fluoxetine tablets. If you would like more information, talk with your healthcare provider. You may ask your healthcare provider or pharmacist for information about fluoxetine tablets that is written for healthcare professionals. For more information about fluoxetine tablets call 1-800-912-9561.

What are the ingredients in fluoxetine tablets?

Active ingredient: fluoxetine hydrochloride, USP

Inactive ingredients: colloidal silicon dioxide, croscarmellose sodium, D&C Yellow No. 10 lake, FD&C Yellow no. 6 lake, magnesium stearate, microcrystalline cellulose, and povidone.

Trade marks are property of their respective owners.

This Medication Guide has been approved by the U.S. Food and Drug Administration.

Manufactured by:

TORRENT PHARMACEUTICALS LTD., INDIA.

Manufactured for:

TORRENT PHARMA INC., Basking Ridge, NJ 07920

8093817 August 2023

PACKAGE LABEL.PRINCIPAL DISPLAY PANEL

Fluoxetine Tablets, USP 10 mg

Fluoxetine Tablets, USP 10 mg (Dahej)

Fluoxetine Tablets, USP 20 mg

Fluoxetine Tablets, USP 20 mg (Dahej)